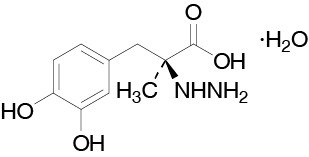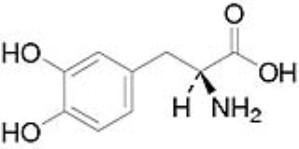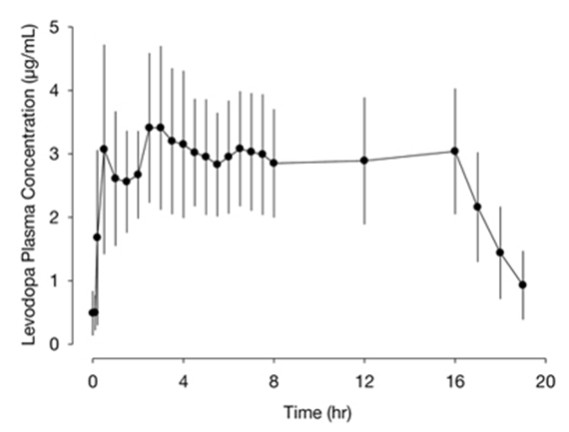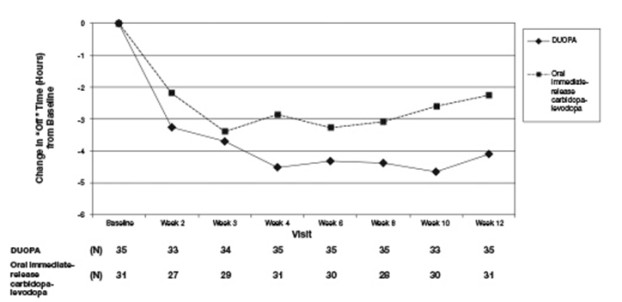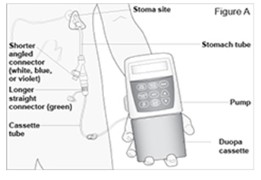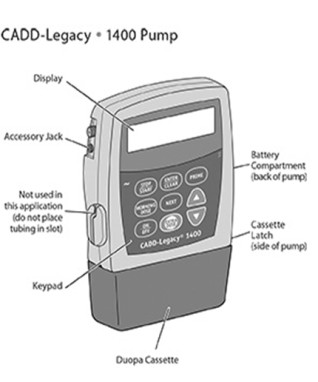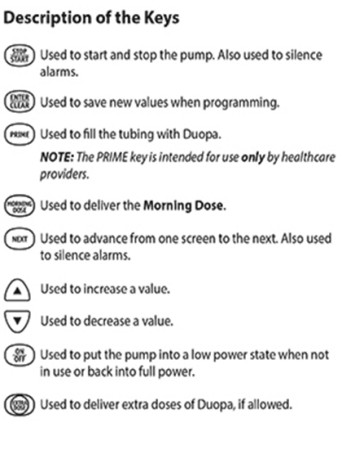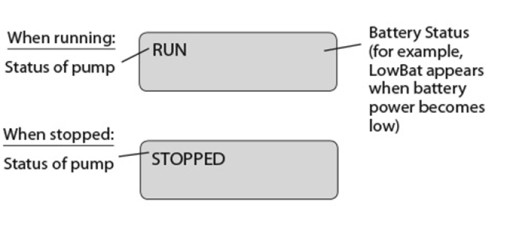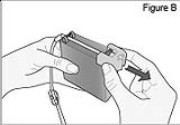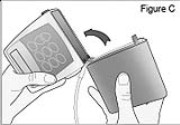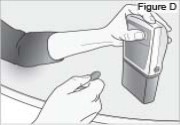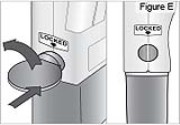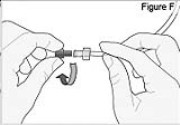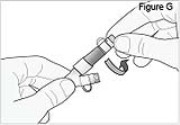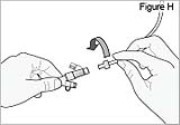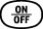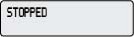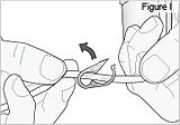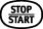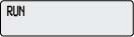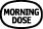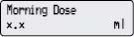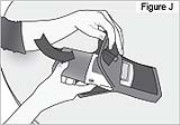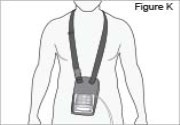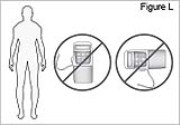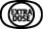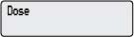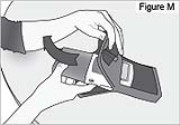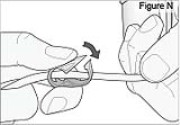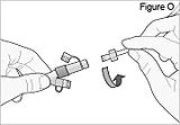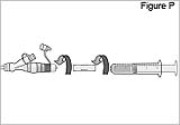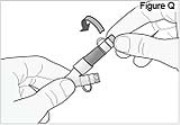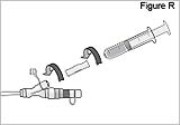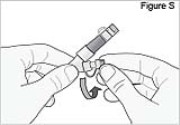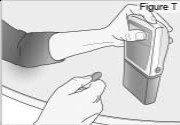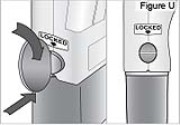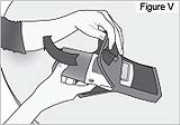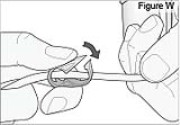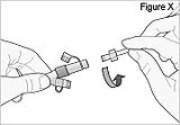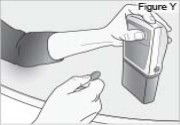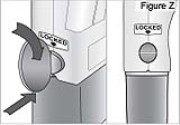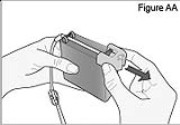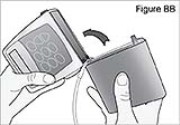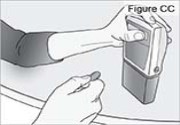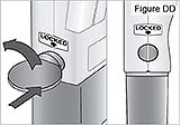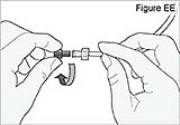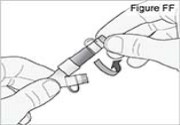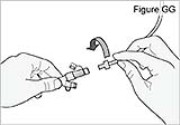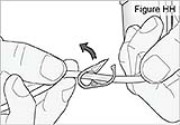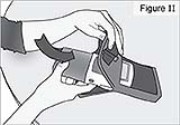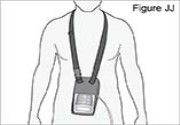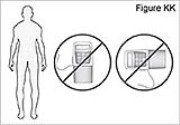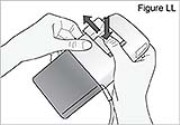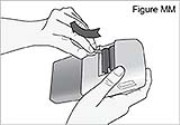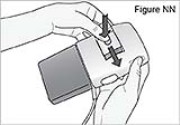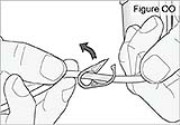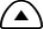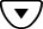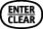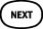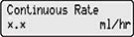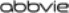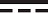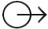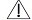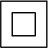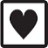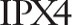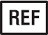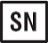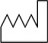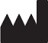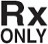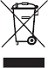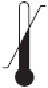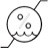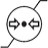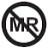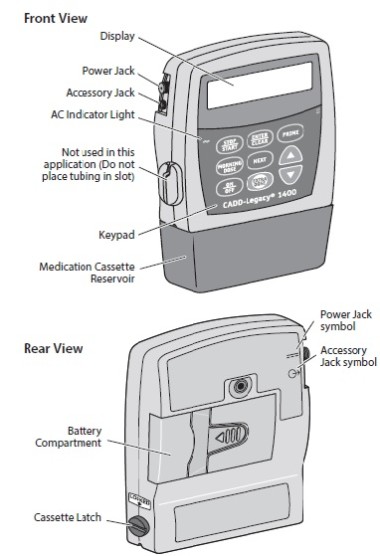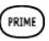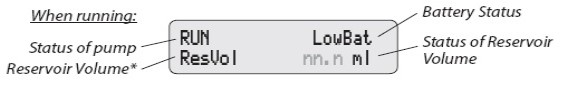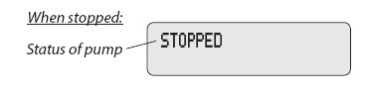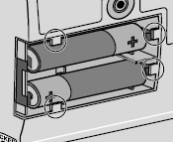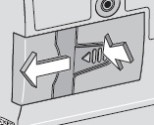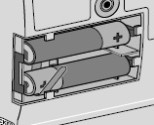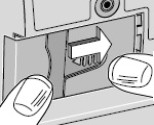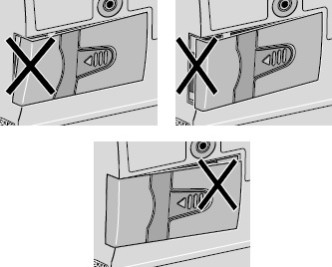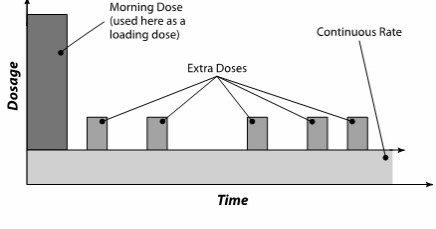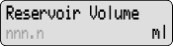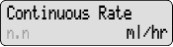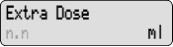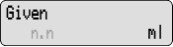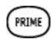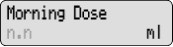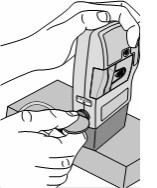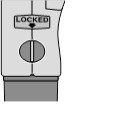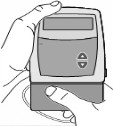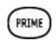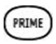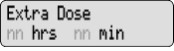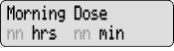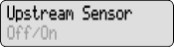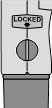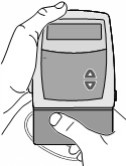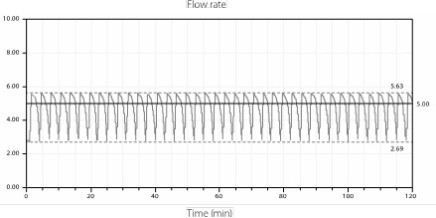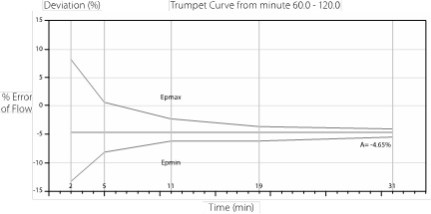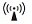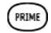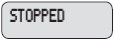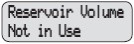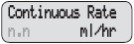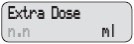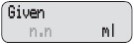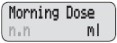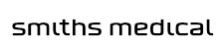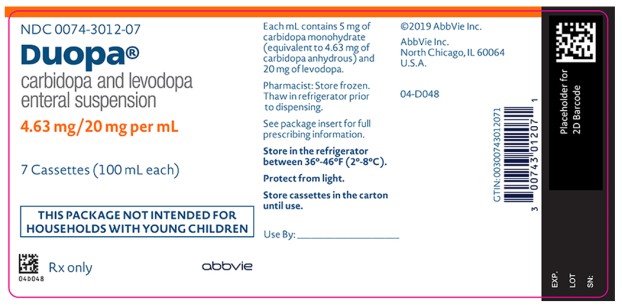 DRUG LABEL: Duopa
NDC: 0074-3012 | Form: SUSPENSION
Manufacturer: AbbVie Inc.
Category: prescription | Type: HUMAN PRESCRIPTION DRUG LABEL
Date: 20250507

ACTIVE INGREDIENTS: Levodopa 20 mg/1 mL; Carbidopa 4.63 mg/1 mL
INACTIVE INGREDIENTS: CARBOXYMETHYLCELLULOSE SODIUM, UNSPECIFIED FORM; WATER

HIGHLIGHTS OF PRESCRIBING INFORMATION

These highlights do not include all the information needed to use DUOPA safely and effectively. See full prescribing information for DUOPA.
DUOPA® (carbidopa and levodopa) enteral suspension
Initial U.S. Approval: 1975

1 INDICATIONS AND USAGE

DUOPA is a combination of carbidopa (an aromatic amino acid decarboxylation inhibitor) and levodopa (an aromatic amino acid) indicated for the treatment of motor fluctuations in patients with advanced Parkinson’s disease (1)

2 DOSAGE AND ADMINISTRATION

- The maximum recommended daily dose of DUOPA is 2000 mg of levodopa (i.e., one cassette per day) administered over 16 hours (2.1)
- Prior to initiating DUOPA, convert patients from all forms of levodopa to oral immediate-release carbidopa-levodopa tablets (1:4 ratio) (2.2)
- Titrate total daily dose based on clinical response for the patient (2.2)
- Administer DUOPA into the jejunum through a percutaneous endoscopic gastrostomy with jejunal tube (PEG-J) with the CADD®-Legacy 1400 portable infusion pump (2.3)

3 DOSAGE FORMS AND STRENGTHS

Enteral Suspension: 4.63 mg carbidopa and 20 mg levodopa per mL (3)

4 CONTRAINDICATIONS

DUOPA is contraindicated in patients taking nonselective monoamine oxidase (MAO) inhibitors (4)

5 WARNINGS AND PRECAUTIONS

- Gastrointestinal procedure-related complications may result in serious outcomes, such as need for surgery or death (5.1)
- May cause falling asleep during activities of daily living (5.2)
- Monitor patients for orthostatic hypotension, especially after starting DUOPA or increasing the dose (5.3)
- Hallucinations/Psychosis/Confusion: May respond to dose reduction in levodopa (5.4)
- Impulse Control Disorders: Consider dose reductions or stopping DUOPA (5.5)
- Monitor patients for depression and suicidality (5.6)
- Avoid sudden discontinuation or rapid dose reduction to reduce the risk of withdrawal-emergent hyperpyrexia and confusion (5.7)
- May cause or exacerbate dyskinesia: Consider dose reduction (5.8)
- Monitor patients for signs and symptoms of peripheral neuropathy (5.9)

6 ADVERSE REACTIONS

Most common adverse reactions for DUOPA (DUOPA incidence at least 7% greater than oral carbidopa-levodopa incidence) were: complication of device insertion, nausea, depression, peripheral edema, hypertension, upper respiratory tract infection, oropharyngeal pain, atelectasis, and incision site erythema. (6.1)

To report SUSPECTED ADVERSE REACTIONS, contact AbbVie Inc. at 1-800-633-9110 or FDA at 1-800-FDA-1088 or www.fda.gov/medwatch.

7 DRUG INTERACTIONS

- Selective MAO-B inhibitors: May cause orthostatic hypotension (7.1)
- Antihypertensive drugs: May cause symptomatic postural hypotension. Dosage adjustment of the antihypertensive drug may be needed (7.2)
- Dopamine D2 receptor antagonists, isoniazid, iron salts, and high-protein diet may reduce the effectiveness of DUOPA (7.3, 7.4, 7.5)

8 USE IN SPECIFIC POPULATIONS

Pregnancy: Based on animal data, may cause fetal harm (8.1)

FULL PRESCRIBING INFORMATION

1 INDICATIONS AND USAGE

DUOPA® is indicated for the treatment of motor fluctuations in patients with advanced Parkinson’s disease.

2 DOSAGE AND ADMINISTRATION

2.1 DUOPA Daily Dose

DUOPA is administered over a 16-hour infusion period. The daily dose is determined by individualized patient titration and composed of:

- A Morning Dose
- A Continuous Dose
- Extra Doses

The maximum recommended daily dose of DUOPA is 2000 mg of the levodopa component (i.e., one cassette per day) administered over 16 hours. At the end of the daily 16-hour infusion, patients will disconnect the pump from the PEG-J and take their night-time dose of oral immediate-release carbidopa-levodopa tablets.

Treatment with DUOPA is initiated in 3 steps [see Dosage and Administration (2.2)]:

1. Conversion of patients to oral immediate-release carbidopa-levodopa tablets in preparation for DUOPA treatment.
2. Calculation and administration of the DUOPA starting dose (Morning Dose and Continuous Dose) for Day 1.
3. Titration of the dose as needed based on individual clinical response and tolerability.

Extra Doses

DUOPA has an extra dose function that can be used to manage acute “Off” symptoms that are not controlled by the Morning Dose and the Continuous Dose administered over 16 hours. The extra dose function should be set at 1 mL (20 mg of levodopa) when starting DUOPA. If the amount of the extra dose needs to be adjusted, it is typically done in 0.2 mL increments. The extra dose frequency should be limited to one extra dose every 2 hours. Administration of frequent extra doses may cause or worsen dyskinesias.

Once no further adjustments are required to the DUOPA Morning Dose, Continuous Dose, or Extra Dose, this dosing regimen should be administered daily. Over time, additional changes may be necessary based on the patient’s clinical response and tolerability.

2.2 Initiation and Titration Instructions

Prepare for DUOPA Treatment

Prior to initiating DUOPA, convert patients from all other forms of levodopa to oral immediate-release carbidopa-levodopa tablets (1:4 ratio). Patients should remain on a stable dose of their concomitant medications taken for the treatment of Parkinson's disease before initiation of DUOPA infusion.

Healthcare providers should ensure patients take their oral Parkinson's disease medications the morning of the PEG-J procedure.

Determine the DUOPA Starting Dose for Day 1

The steps for determining the initial DUOPA daily dosing (Morning Dose and Continuous Dose) for Day 1 are outlined below.

Step 1: Calculate and administer the DUOPA Morning Dose for Day 1
a. | Determine the total amount of levodopa (in milligrams) in the first dose of oral immediate-release carbidopa-levodopa that was taken by the patient on the previous day.
b. | Convert the oral levodopa dose from milligrams to milliliters by multiplying the oral dose by 0.8 and dividing by 20 mg/mL. This calculation will provide the Morning Dose of DUOPA in milliliters.
c. | Add 3 milliliters to the Morning Dose to fill (prime) the intestinal tube to obtain the Total Morning Dose.
d. | The Total Morning Dose is usually administered over 10 to 30 minutes.
e. | Program the pump to deliver the Total Morning Dose.
Step 2: Calculate and administer the DUOPA Continuous Dose for Day 1
a. | Determine the amount of oral immediate-release levodopa that the patient received from oral immediate-release carbidopa-levodopa doses throughout the previous day (16 waking hours), in milligrams. Do not include the doses of oral immediate-release carbidopa-levodopa taken at night when calculating the levodopa amount.
b. | Subtract the first oral levodopa dose in milligrams taken by the patient on the previous day (determined in Step 1 (a)) from the total oral levodopa dose in milligrams taken over 16 waking hours (determined in Step 2 (a)). Divide the result by 20 mg/mL. This is the dose of DUOPA administered as a Continuous Dose (in mL) over 16 hours.
c. | The hourly infusion rate (mL per hour) is obtained by dividing the Continuous Dose by 16 (hours). This value will be programmed into the pump as the continuous rate.
d. | If persistent or numerous “Off” periods occur during the 16-hour infusion, consider increasing the Continuous Dose or using the Extra Dose function. If dyskinesia or DUOPA-related adverse reactions occur, consider decreasing the Continuous Dose or stopping the infusion until the adverse reactions subside.

DUOPA Titration

The daily dose of DUOPA can be titrated as needed, based on the patient’s individual clinical response and tolerability after Day 1 of DUOPA treatment and until a stable daily dose is maintained. Adjustments to concomitant Parkinson’s disease medications may be needed. In the controlled trial, the average number of titration days required to establish a stable Morning and Continuous Dose was 5 days. Additional dose adjustments may be necessary over time based on the patient level of activity and disease progression.

The recommendations for adjusting the DUOPA Morning and Continuous Doses are provided below.

Morning Dose Adjustment

If there was an inadequate clinical response within 1 hour of the Morning Dose on the preceding day, adjust the Morning Dose (excluding the 3 mL to fill the tube) as follows:

- If the Morning Dose on the preceding day was less than or equal to 6 mL, increase the Morning Dose by 1 mL.
- If the Morning Dose on the preceding day was greater than 6 mL, increase the Morning Dose by 2 mL.

If the patient experienced dyskinesias or DUOPA-related adverse reactions within 1 hour of the Morning Dose on the preceding day, decrease the Morning Dose by 1 mL.

Continuous Dose Adjustment

Consider increasing the Continuous Dose based on the number and volume of Extra Doses of DUOPA (i.e., total amount of levodopa component) that were needed for the previous day and the patient’s clinical response.

Consider decreasing the Continuous Dose if the patient experienced troublesome dyskinesia, or other troublesome DUOPA-related adverse reactions on the preceding day:

- For troublesome adverse reactions lasting for a period of one hour or more, decrease the Continuous Dose by 0.3 mL per hour.
- For troublesome adverse reactions lasting for two or more periods of one hour or more, decrease the Continuous Dose by 0.6 mL per hour.

2.3 Administration Information

- DUOPA should be used at room temperature. Take one DUOPA cassette out of the refrigerator and out of the carton 20 minutes prior to use; failure to use the product at room temperature may result in the patient not receiving the right amount of medication.
- DUOPA is delivered as a 16-hour infusion through either a naso-jejunal tube for short-term administration or through a PEG-J for long-term administration.
- The cassettes are for single-use only and should not be used for longer than 16 hours, even if some drug product remains.
- An opened cassette should not be re-used.
- The PEG-J should be disconnected from the pump at the end of the daily 16-hour administration period and flushed with room temperature potable water with a syringe.

Long-term administration of DUOPA requires placement of a PEG-J outer transabdominal tube and inner jejunal tube by percutaneous endoscopic gastrostomy. DUOPA is dispensed from medication cassette reservoirs that are specifically designed to be connected to the CADD®-Legacy 1400 pump.

Establishment of the transabdominal port should be performed by a gastroenterologist or other healthcare provider experienced in this procedure. See Table 1 for the recommended tubing sets for PEG-J administration.

For short-term, temporary administration of DUOPA prior to PEG-J tube placement, treatment may be initiated by a naso-jejunal tube with observation of the patient’s clinical response. See Table 2 for the recommended tubing sets for naso-jejunal administration.

Table 1. Recommended Tubing Sets for Long-Term PEG-J DUOPA Administration
Product Name | Manufacturer
AbbVie PEG 15 and 20 Fr AbbVie J | AbbVie Inc. AbbVie Inc.

Table 2. Recommended Tubing Sets for Short-Term Naso-Jejunal DUOPA Administration
Product Name | Manufacturer
AbbVie NJ | AbbVie Inc.
NJFT-10 | Wilson-Cook Medical, Inc.
Kangaroo™ Naso-Jejunal Feeding Tube | Covidien
Kangaroo™ | Covidien

2.4 Discontinuation of DUOPA

Avoid sudden discontinuation or rapid dose reduction in patients taking DUOPA.

If patients need to discontinue DUOPA, the dose should be tapered or patients should be switched to oral immediate-release carbidopa-levodopa tablets [see Warnings and Precautions (5.7)].

When using a PEG-J tube, DUOPA can be discontinued by withdrawing the tube and letting the stoma heal. The removal of the tube should only be performed by a qualified healthcare provider.

3 DOSAGE FORMS AND STRENGTHS

Enteral suspension: 4.63 mg carbidopa and 20 mg levodopa per mL in a single-use cassette. Each cassette contains approximately 100 mL of suspension.

4 CONTRAINDICATIONS

DUOPA is contraindicated in patients who are currently taking a nonselective monoamine oxidase (MAO) inhibitor (e.g., phenelzine and tranylcypromine) or have recently (within 2 weeks) taken a nonselective MAO inhibitor. Hypertension can occur if these drugs are used concurrently [see Drug Interactions (7.1 and 7.2)].

5 WARNINGS AND PRECAUTIONS

5.1 Gastrointestinal and Gastrointestinal Procedure-Related Risks

Because DUOPA is administered using a PEG-J or naso-jejunal tube, gastrointestinal complications can occur.

These complications include abscess, bezoar, ileus, implant site erosion/ulcer, intestinal hemorrhage, intestinal ischemia, intestinal obstruction, intestinal perforation, intussusception, pancreatitis, peritonitis, pneumonia (including aspiration pneumonia), pneumoperitoneum, post-operative wound infection, and sepsis. These complications may result in serious outcomes, such as the need for surgery or death.

Instruct patients to notify their healthcare provider immediately if they experience abdominal pain, prolonged constipation, nausea, vomiting, fever, or melanotic stool [see Patient Counseling Information (17)].

5.2 Falling Asleep During Activities of Daily Living and Somnolence

Patients treated with levodopa, a component of DUOPA, have reported falling asleep while engaged in activities of daily living, including the operation of motor vehicles, which sometimes resulted in accidents. Although many of these patients reported somnolence while on levodopa, some perceived that they had no warning signs (sleep attack), such as excessive drowsiness, and believed that they were alert immediately prior to the event. Some of these events have been reported more than one year after initiation of treatment.

Falling asleep while engaged in activities of daily living usually occurs in patients experiencing preexisting somnolence, although patients may not give such a history. For this reason, prescribers should reassess patients for drowsiness or sleepiness in DUOPA-treated patients, especially since some of the events occur well after the start of treatment. Prescribers should be aware that patients may not acknowledge drowsiness or sleepiness until directly questioned about drowsiness or sleepiness during specific activities. Patients who have already experienced somnolence or an episode of sudden sleep onset should not participate in these activities while taking DUOPA.

Before initiating treatment with DUOPA, advise patients about the potential to develop drowsiness and specifically ask about factors that may increase the risk for somnolence with DUOPA such as the use of concomitant sedating medications or the presence of sleep disorders. Consider discontinuing DUOPA in patients who report significant daytime sleepiness or episodes of falling asleep during activities that require active participation (e.g., conversations, eating). If DUOPA is continued, they should be advised to avoid driving and other potentially dangerous activities that might result in harm if the patient becomes somnolent.

5.3 Orthostatic Hypotension

DUOPA-treated patients were more likely to experience a decline in orthostatic blood pressure than patients treated with oral immediate-release carbidopa-levodopa in the controlled clinical study. Orthostatic systolic hypotension (≥30 mm Hg decrease) occurred in 73% of DUOPA-treated patients compared to 68% of patients treated with oral immediate-release carbidopa-levodopa in the controlled clinical study. Orthostatic diastolic hypotension (≥20 mm Hg decrease) occurred in 70% of DUOPA-treated patients compared to 62% of patients treated with oral immediate-release carbidopa-levodopa. Inform patients about the risk for hypotension and syncope. Monitor patients for orthostatic hypotension, especially after starting DUOPA or increasing the dose.

5.4 Hallucinations/Psychosis/Confusion

There is an increased risk for hallucinations and psychosis in patients taking DUOPA. In the controlled clinical trial, hallucinations occurred in 5% of DUOPA-treated patients compared to 3% of patients treated with oral immediate-release carbidopa-levodopa. Confusion occurred in 8% of DUOPA-treated patients compared to 3% of patients treated with oral immediate-release carbidopa-levodopa, and psychotic disorder occurred in 5% of DUOPA-treated patients compared to 3% of patients treated with oral immediate-release carbidopa-levodopa.

Hallucinations associated with levodopa may present shortly after the initiation of therapy and may be responsive to dose reduction in levodopa. Confusion, insomnia, and excessive dreaming may accompany hallucinations. Abnormal thinking and behavior may present with one or more symptoms, including paranoid ideation, delusions, hallucinations, confusion, psychosis, disorientation, aggressive behavior, agitation, and delirium.

Because of the risk of exacerbating psychosis, patients with a major psychotic disorder should not be treated with DUOPA. In addition, medications that antagonize the effects of dopamine used to treat psychosis may exacerbate the symptoms of Parkinson’s disease and may decrease the effectiveness of DUOPA [see Drug Interactions (7.3)].

5.5 Impulse Control/Compulsive Behaviors

Patients may experience intense urges to gamble, increased sexual urges, intense urges to spend money, binge or compulsive eating, and/or other intense urges, and the inability to control these urges while taking one or more of the medications, including DUOPA, that increase central dopaminergic tone and that are generally used for the treatment of Parkinson’s disease. In some cases, although not all, these urges were reported to have stopped when the dose was reduced or the medication was discontinued.

Because patients may not recognize these behaviors as abnormal, it is important for prescribers to ask patients or their caregivers specifically about the development of new or increased gambling urges, sexual urges, uncontrolled spending, binge or compulsive eating, or other urges while being treated with DUOPA. Consider reducing the dose or discontinuing DUOPA if a patient develops such urges.

5.6 Depression and Suicidality

In the controlled clinical trial, 11% of DUOPA-treated patients developed depression compared to 3% of oral immediate-release carbidopa-levodopa-treated patients.

Monitor patients for the development of depression and concomitant suicidal tendencies.

5.7 Withdrawal-Emergent Hyperpyrexia and Confusion

A symptom complex that resembles neuroleptic malignant syndrome (characterized by elevated temperature, muscular rigidity, altered consciousness, and autonomic instability), with no other obvious etiology, has been reported in association with rapid dose reduction, withdrawal of, or changes in dopaminergic therapy. Avoid sudden discontinuation or rapid dose reduction in patients taking DUOPA. If DUOPA is discontinued, the dose should be tapered to reduce the risk of hyperpyrexia and confusion [see Dosage and Administration (2.4)].

5.8 Dyskinesia

DUOPA may cause or exacerbate dyskinesias. In the controlled clinical trial, dyskinesia occurred in 14% of DUOPA-treated patients compared to 12% of patients treated with oral immediate-release carbidopa-levodopa. The occurrence of dyskinesias may require a dosage reduction of DUOPA or other medications used to treat Parkinson’s disease.

5.9 Neuropathy

In clinical studies, 19 of 412 (5%) patients treated with DUOPA developed a generalized polyneuropathy. The onset of neuropathy could be determined in 13 of 19 patients. Most cases (12/19) were classified as subacute or chronic in onset. The neuropathy was most often characterized as sensory or sensorimotor. Electrodiagnostic testing performed in 16 patients was most often (15/16) consistent with an axonal polyneuropathy, and one patient was classified as having a demyelinating neuropathy. There was insufficient information to determine the potential role of vitamin deficiencies in the etiology of neuropathy associated with DUOPA.

Patients should have clinical assessments for the signs and symptoms of peripheral neuropathy before starting DUOPA. Monitor patients periodically for signs of neuropathy after starting DUOPA, especially in patients with pre-existing neuropathy and in patients taking medications or those who have medical conditions that are also associated with neuropathy.

5.10 Cardiovascular Ischemic Events

In clinical studies, myocardial infarction and arrhythmia were reported in patients taking carbidopa-levodopa. Ask patients about symptoms of ischemic heart disease and arrhythmia, especially those with a history of myocardial infarction or cardiac arrhythmias.

5.11 Laboratory Test Abnormalities

DUOPA may increase the risk for elevated (above the upper limit of normal for the reference range) blood urea nitrogen (BUN) and creatine phosphokinase (CPK). In the controlled clinical trial, the shift from a low or normal value at baseline to an increased BUN value was greater for DUOPA-treated patients (13%) than for patients treated with oral immediate-release carbidopa-levodopa (4%). The shift from a low or normal value at baseline to an increased CPK value was greater for DUOPA-treated patients (17%) than for patients treated with oral immediate-release carbidopa-levodopa (7%). The incidence of patients with a markedly increased BUN (≥10 mmol/L; ≥28 mg/dL) was greater for patients treated with DUOPA (11%) than that for patients treated with oral immediate-release carbidopa-levodopa (0%). The incidence of patients with an increased CPK (>3 times the upper limit of normal) was greater for patients treated with DUOPA (9%) than that for patients treated with oral immediate-release carbidopa-levodopa (0%).

Patients taking levodopa or carbidopa-levodopa may have increased levels of catecholamines and their metabolites in plasma and urine giving false positive results suggesting the diagnosis of pheochromocytoma in patients on levodopa and carbidopa-levodopa.

5.12 Glaucoma

Carbidopa-levodopa may cause increased intraocular pressure in patients with glaucoma. Monitor intraocular pressure in patients with glaucoma after starting DUOPA.

6 ADVERSE REACTIONS

The following serious adverse reactions are discussed below and elsewhere in labeling:

- Gastrointestinal and Gastrointestinal Procedure-Related Risks [see Warnings and Precautions (5.1)]
- Falling Asleep During Activities of Daily Living and Somnolence [see Warnings and Precautions (5.2)]
- Orthostatic Hypotension [see Warnings and Precautions (5.3)]
- Hallucinations/Psychosis/Confusion [see Warnings and Precautions (5.4)]
- Impulse Control/Compulsive Behaviors [see Warnings and Precautions (5.5)]
- Depression and Suicidality [see Warnings and Precautions (5.6)]
- Withdrawal-Emergent Hyperpyrexia and Confusion [see Warnings and Precautions (5.7)]
- Dyskinesia [see Warnings and Precautions (5.8)]
- Neuropathy [see Warnings and Precautions (5.9)]
- Cardiovascular Ischemic Events [see Warnings and Precautions (5.10)]
- Laboratory Test Abnormalities [see Warnings and Precautions (5.11)]
- Glaucoma [see Warnings and Precautions (5.12)]

6.1 Clinical Trials Experience

Because clinical studies are run under widely varying conditions, the incidence of adverse reactions observed in the clinical trials of a drug cannot be directly compared to rates in the clinical trials of another drug and may not reflect the rates observed in practice.

In clinical studies, 416 patients with advanced Parkinson’s disease received DUOPA. 338 patients were treated with DUOPA for more than 1 year, 233 patients were treated with DUOPA for more than 2 years, and 162 patients were treated with DUOPA for more than 3 years.

In a 12-week, active-controlled clinical trial (Study 1), a total of 71 patients with advanced Parkinson’s disease were enrolled and had a PEG-J procedure. Of these, 37 patients received DUOPA and 34 received oral immediate-release carbidopa-levodopa.

The most common adverse reactions for DUOPA (incidence at least 7% greater than oral immediate-release carbidopa-levodopa) were: complication of device insertion, nausea, depression, peripheral edema, hypertension, upper respiratory tract infection, oropharyngeal pain, atelectasis, and incision site erythema.

Table 3 lists the incidence of adverse reactions occurring in the DUOPA-treated group (requiring at least 2 patients in this group) in Study 1 when the incidence was numerically greater than that for oral immediate-release carbidopa-levodopa.

Table 3. Adverse Reactions in Study 1 for DUOPA in Patients with Advanced Parkinson’s disease
Preferred Term | DUOPA (n = 37) % | Oral immediate-release carbidopa-levodopaa (n = 34) %
Complication of device insertion | 57 | 44
Nausea | 30 | 21
Constipation | 22 | 21
Incision site erythema | 19 | 12
Dyskinesia | 14 | 12
Depression | 11 | 3
Post procedural discharge | 11 | 9
Peripheral edema | 8 | 0
Hypertension | 8 | 0
Upper respiratory tract infection | 8 | 0
Oropharyngeal pain | 8 | 0
Atelectasis | 8 | 0
Confusional state | 8 | 3
Anxiety | 8 | 3
Dizziness | 8 | 6
Hiatal hernia | 8 | 6
Postoperative ileus | 5 | 0
Sleep disorder | 5 | 0
Pyrexia | 5 | 0
Excessive granulation tissue | 5 | 0
Rash | 5 | 0
Bacteriuria | 5 | 0
White blood cells urine positive | 5 | 0
Hallucination | 5 | 3
Psychotic disorder | 5 | 3
Diarrhea | 5 | 3
Dyspepsia | 5 | 3
aAll patients in the clinical trial regardless of treatment arm received a PEG-J.

Procedure and Device- Related Adverse Reactions

The most common adverse reactions associated with complications due to naso-jejunal (NJ) insertion were: oropharyngeal pain, abdominal distention, abdominal pain, abdominal discomfort, pain, throat irritation, gastrointestinal injury, esophageal hemorrhage, anxiety, dysphagia, and vomiting.

The most common adverse reactions associated with complications due to PEG-J insertion were: abdominal pain, abdominal discomfort, abdominal distension, flatulence, or pneumoperitoneum.

Additional adverse reactions that were co-reported with complication of naso-jejunal and PEG-J insertion included upper abdominal pain, duodenal ulcer, duodenal ulcer hemorrhage, erosive duodenitis, erosive gastritis, gastrointestinal hemorrhage, intussusception, peritonitis, post-operative abscess, and small intestine ulcer.

7 DRUG INTERACTIONS

7.1 Monoamine Oxidase (MAO) Inhibitors

The use of nonselective MAO inhibitors with DUOPA is contraindicated [see Contraindications (4)]. Discontinue use of any nonselective MAO inhibitors at least two weeks prior to initiating DUOPA.

The use of selective MAO-B inhibitors (e.g., rasagiline and selegiline) with DUOPA may be associated with orthostatic hypotension. Monitor patients who are taking these drugs.

7.2 Antihypertensive Drugs

The concurrent use of DUOPA with antihypertensive medications can cause symptomatic postural hypotension. A dose reduction of the antihypertensive medication may be needed after starting or increasing the dose of DUOPA.

7.3 Dopamine D2 Receptor Antagonists and Isoniazid

Dopamine D2 receptor antagonists (e.g., phenothiazines, butyrophenones, risperidone, metoclopramide, papaverine) and isoniazid may reduce the effectiveness of levodopa. Monitor patients for worsening Parkinson’s symptoms.

7.4 Iron Salts

Iron salts or multi-vitamins containing iron salts can form chelates with levodopa, carbidopa, and can cause a reduction in the bioavailability of DUOPA. If iron salts or multi-vitamins containing iron salts are co-administered with DUOPA, monitor patients for worsening Parkinson’s symptoms.

7.5 High-Protein Diet

Because levodopa competes with certain amino acids for transport across the gut wall, the absorption of levodopa may be decreased in patients on a high-protein diet. Advise patients that a high-protein diet may reduce the effectiveness of DUOPA.

8 USE IN SPECIFIC POPULATIONS

8.1 Pregnancy

Risk Summary

There are no adequate data on the developmental risk associated with the use of DUOPA in pregnant women. In animal studies, carbidopa-levodopa has been shown to be developmentally toxic (including teratogenic effects) at clinically relevant doses (see Data).

The estimated background risk of major birth defects and miscarriage in the indicated population is unknown. In the U.S. general population, the estimated background risk of major birth defects and miscarriage in clinically recognized pregnancies is 2% to 4% and 15% to 20%, respectively.

Data

Animal Data

When administered to pregnant rabbits throughout organogenesis, carbidopa-levodopa caused both visceral and skeletal malformations in fetuses at all doses and ratios of carbidopa-levodopa tested. No teratogenic effects were observed when carbidopa-levodopa was administered to pregnant mice throughout organogenesis. There was a decrease in the number of live pups delivered by rats receiving carbidopa-levodopa during organogenesis.

8.2 Lactation

Risk Summary

Levodopa has been detected in human milk after administration of carbidopa-levodopa. There are no data on the presence of carbidopa in human milk, the effects of levodopa or carbidopa on the breastfed infant, or the effects on milk production. However, inhibition of lactation may occur because levodopa decreases secretion of prolactin in humans. Carbidopa is excreted in rat milk.

The developmental and health benefits of breastfeeding should be considered along with the mother’s clinical need for DUOPA and any potential adverse effects on the breastfed infant from DUOPA or from the underlying maternal condition.

8.4 Pediatric Use

Safety and effectiveness in pediatric patients have not been established.

8.5 Geriatric Use

In the controlled clinical trial, 49% of patients were 65 years and older, and 8% were 75 years and older. In patients 65 years and older, there was an increased risk for elevation of BUN and CPK (above the upper limit of the normal reference range for these laboratory analytes) during treatment with DUOPA compared to the risk for patients less than 65 years.

10 OVERDOSAGE

Management of acute overdosage with DUOPA is the same as management of acute overdosage with levodopa. Pyridoxine is not effective in reversing the actions of oral immediate-release carbidopa-levodopa.

In the event of an overdosage with DUOPA, the infusion should be stopped and the pump disconnected immediately. Administer intravenous fluids and maintain an adequate airway. Patients should receive electrocardiographic monitoring for arrhythmias and hypotension.

11 DESCRIPTION

DUOPA is a combination of carbidopa, an inhibitor of aromatic amino acid decarboxylation, and levodopa, an aromatic amino acid.

Carbidopa is a white, crystalline compound, slightly soluble in water, with a molecular weight of 244.2. It is designated chemically as (2S)-3-(3,4-dihydroxyphenyl)-2-hydrazino-2-methylpropanoic acid monohydrate. Its empirical formula is C10H14N2O4•H2O, and its structural formula is:

The content of carbidopa in DUOPA is expressed in terms of anhydrous carbidopa which has a molecular weight of 226.3. The 4.63 mg/mL of anhydrous carbidopa is equivalent to 5.0 mg/mL of carbidopa.

Levodopa is a white, crystalline compound, slightly soluble in water, with a molecular weight of 197.2. It is designated chemically as (2S)-2-Amino-3-(3,4-dihydroxyphenyl) propanoic acid. Its empirical formula is C9H11NO4, and its structural formula is:

The inactive ingredients in DUOPA are carmellose sodium and purified water.

12 CLINICAL PHARMACOLOGY

12.1 Mechanism of Action

Carbidopa

When levodopa is administered orally, it is rapidly decarboxylated to dopamine in extracerebral tissues so that only a small portion of a given dose is transported unchanged to the central nervous system. Carbidopa inhibits the decarboxylation of peripheral levodopa, making more levodopa available for delivery to the brain.

Levodopa

Levodopa is the metabolic precursor of dopamine, does cross the blood-brain barrier, and presumably is converted to dopamine in the brain. This is thought to be the mechanism whereby levodopa treats the symptoms of Parkinson's disease.

12.2 Pharmacodynamics

Because its decarboxylase inhibiting activity is limited to extracerebral tissues, administration of carbidopa with levodopa makes more levodopa available to the brain. The addition of carbidopa to levodopa reduces the peripheral effects (e.g., nausea and vomiting) due to decarboxylation of levodopa; however, carbidopa does not decrease the adverse reactions due to the central effects of levodopa.

12.3 Pharmacokinetics

The pharmacokinetics of carbidopa and levodopa with 16-hour intrajejunal infusion of DUOPA was evaluated in 18 patients with advanced Parkinson's disease who had been on DUOPA therapy for 30 days or longer. Patients remained on their individualized DUOPA doses.

The plasma concentrations versus time profile for levodopa with DUOPA 16-hour intrajejunal infusion is presented in Figure 1.

Figure 1. Plasma Concentrations (mean ± standard deviation) versus Time Profile of Levodopa with DUOPA (levodopa, 1580 ± 403 mg; carbidopa, 366 ± 92 mg) 16-Hour Infusion

Absorption and Bioavailability

Following initiation of the 16-hour intrajejunal infusion of DUOPA, peak plasma levels of levodopa is reached at 2.5 hours. The absorption of levodopa may be decreased in patients on a high-protein diet because levodopa competes with certain amino acids for transport across the gut wall. The gastric emptying rate does not influence the absorption of DUOPA since it is administered by continuous intestinal infusion. In a cross-study population pharmacokinetic analysis, DUOPA had comparable bioavailability to the oral immediate-release carbidopa-levodopa (25/100 mg) tablets (over-encapsulated tablets). The estimated bioavailability for levodopa from DUOPA relative to oral immediate-release carbidopa-levodopa tablets was 97% (95% confidence interval; 95% to 98%).

In the controlled clinical trial, the intra-subject variability in carbidopa and levodopa plasma concentrations were lower for patients treated with DUOPA (N=33, 25% and 21%, respectively) than in patients treated with oral immediate-release carbidopa-levodopa (25/100 mg) tablets (N=28, 39% and 67%, respectively).

Distribution

Carbidopa is approximately 36% bound to plasma proteins. Levodopa is approximately 10-30% bound to plasma proteins.

Metabolism and Elimination

Carbidopa

Carbidopa is metabolized to two main metabolites (α-methyl-3-methoxy-4-hydroxyphenylpropionic acid and α-methyl-3,4-dihydroxyphenylpropionic acid). These 2 metabolites are primarily eliminated in the urine unchanged or as glucuronide conjugates. Unchanged carbidopa accounts for 30% of the total urinary excretion. The elimination half-life of carbidopa is approximately 2 hours.

Levodopa

Levodopa is mainly eliminated via metabolism by the aromatic amino acid decarboxylase (AAAD) and the catechol-O-methyl-transferase (COMT) enzymes. Other routes of metabolism are transamination and oxidation. The decarboxylation of levodopa to dopamine by AAAD is the major enzymatic pathway when no enzyme inhibitor is co-administered. O-methylation of levodopa by COMT forms 3-O-methyldopa. When administered with carbidopa, the elimination half-life of levodopa is approximately 1.5 hours (see Figure 1).

Drug Interaction Studies

COMT Inhibitors

Systemic exposure of levodopa is expected to increase in the presence of entacapone.

13 NONCLINICAL TOXICOLOGY

13.1 Carcinogenesis, Mutagenesis, Impairment of Fertility

Carcinogenesis

In rat, oral administration of carbidopa-levodopa for two years resulted in no evidence of carcinogenicity. DUOPA contains hydrazine, a degradation product of carbidopa. In published studies, hydrazine has been demonstrated to be carcinogenic in multiple animal species. Increases in liver (adenoma, carcinoma) and lung (adenoma, adenocarcinoma) tumors have been reported with oral administration of hydrazine in mouse, rat, and hamster.

Mutagenesis

Carbidopa was positive in the in vitro Ames test, in the presence and absence of metabolic activation, and the in vitro mouse lymphoma tk assay in the absence of metabolic activation but was negative in the in vivo mouse micronucleus assay.

In published studies, hydrazine was reported to be positive in in vitro genotoxicity (Ames, chromosomal aberration in mammalian cells, and mouse lymphoma tk) assays and in the in vivo mouse micronucleus assay.

Impairment of Fertility

In reproduction studies, no effects on fertility were observed in rats receiving carbidopa-levodopa.

14 CLINICAL STUDIES

The efficacy of DUOPA was established in a randomized, double-blind, double-dummy, active-controlled, parallel group, 12-week study (Study 1) in patients with advanced Parkinson's disease who were levodopa-responsive and had persistent motor fluctuations while on treatment with oral immediate-release carbidopa-levodopa and other Parkinson's disease medications.

Patients were eligible for participation in the studies if they were experiencing 3 hours or more of “Off” time on their current Parkinson's disease drug treatment and they demonstrated a clear responsiveness to treatment with levodopa. Seventy-one (71) patients enrolled in the study and 66 patients completed the treatment (3 patients discontinued treatment because of adverse reactions, 1 patient for lack of effect, and 1 patient for non-compliance).

Patients enrolled in this study had a mean age of 64 years and disease duration of 11 years. Most patients (89%) were taking at least one concomitant medication for Parkinson’s disease (e.g., dopaminergic agonist, COMT-inhibitor, MAO-B inhibitor) in addition to oral immediate-release carbidopa-levodopa. Thirty nine percent of patients were taking two or more of such concomitant medications.

Patients were randomized to either DUOPA and placebo capsules or placebo suspension and oral immediate-release carbidopa-levodopa 25/100 mg capsules. Patients in both treatment arms had a PEG-J device placement. DUOPA or placebo-suspension was infused over 16 hours daily through a PEG-J tube via the CADD®-Legacy 1400 model ambulatory infusion pump. The mean daily levodopa dose was 1117 mg/day in the DUOPA group and 1351 mg/day in the oral immediate-release carbidopa-levodopa group.

The clinical outcome measure in Study 1 was the mean change from baseline to Week 12 in the total daily mean “Off” time, based on a Parkinson's disease diary. The "Off" time was normalized to a 16-hour awake period, based on a typical person's waking day and the daily infusion duration of 16 hours. The mean score decrease (i.e., improvement) in “Off” time from baseline to Week 12 for DUOPA was significantly greater (p=0.0015) than for oral immediate-release carbidopa-levodopa. Additionally, the mean score increase (i.e., improvement) in “On” time without troublesome dyskinesia from baseline to Week 12 was significantly greater (p=0.0059) for DUOPA than for oral immediate-release carbidopa-levodopa. The treatment difference (DUOPA – oral immediate release carbidopa-levodopa) for decrease in “Off” time was approximately 1.9 hours and the treatment difference for the increase in “On” time without troublesome dyskinesia was approximately 1.9 hours. Results of Study 1 are shown in Table 4.

Table 4. Change from Baseline to Week 12 in "Off" Time and in "On" Time Without Troublesome Dyskinesia in Patients with Advanced Parkinson’s Disease
Treatment Group | Baseline (hours) | LS Mean Change from Baseline at Week 12 (hours)
"Off" time
Oral immediate-release carbidopa-levodopa | 6.9 | -2.1
DUOPA | 6.3 | -4.0*
"On" time without troublesome dyskinesia
Oral immediate-release carbidopa-levodopa | 8.0 | 2.2
DUOPA | 8.7 | 4.1*
LS Mean Change from Baseline based on Analysis of Covariance (ANCOVA).
*=Statistically Significant.

Figure 2 shows results over time according to treatment for the efficacy variable (change from baseline in “Off” time) that served as the clinical outcome measure at the end of the trial at 12 weeks.

Figure 2. Change in “Off” Time Over 12 Weeks.

16 HOW SUPPLIED/STORAGE AND HANDLING

16.1 How Supplied

Single-use cassettes containing 4.63 mg carbidopa (as 5 mg of the monohydrate) and 20 mg levodopa per mL of enteral suspension. Each cassette contains approximately 100 mL of suspension.

Carton of 7 DUOPA cassettes: NDC 0074-3012-07

16.2 Storage and Handling

Store in freezer at -20oC (-4oF). Thaw in refrigerator at 2oC to 8oC (36oF to 46oF) prior to dispensing. Cassettes should be protected from light and kept in the carton prior to use.

Thawing instructions for pharmacies

- Assign a 15 week “Use By” date based on the time the cartons are put into the refrigerator to thaw.
- Fully thaw DUOPA in the refrigerator prior to dispensing.
- In order to ensure controlled thawing of DUOPA, take the cartons containing the seven individual cassettes out of the transport box and separate the cartons from each other.
- Thawing may take up to 96 hours when the cartons are taken out of the transport box.
- Once the product has thawed, the individual cartons may be packed in a closer configuration within the refrigerator.

17 PATIENT COUNSELING INFORMATION

Advise the patient to read the FDA-approved patient labeling (Medication Guide and Instructions for Use).

Administration Information

Ask patients if they have had any previous surgery in the upper part of their abdomen that may lead to difficulty in performing the gastrostomy or jejunostomy [see Dosage and Administration (2.3)].

Advise patients that foods that are high in protein may reduce the effectiveness of DUOPA [see Drug Interactions (7.5) and Clinical Pharmacology (12.3)].

Interruption of DUOPA Infusion

If the patient anticipates disconnecting the pump for a short period of time (less than 2 hours such as to swim, shower, or short medical procedure), no supplemental oral medication is needed, but the patient may be advised to take an extra-dose of DUOPA before disconnecting. Instruct the patient to stop the continuous rate, turn off the pump, clamp the cassette tube, disconnect the tubing, and replace the red cap on the cassette tube. The DUOPA cassette can remain attached to the pump until the tubing is reconnected. Refer the patient to the Patient Instructions for Use for additional information (i.e., changing the DUOPA Cassette: disconnecting Steps 1-5 and reconnecting Steps 10-16).

Advise the patient to contact their healthcare provider and to take oral carbidopa-levodopa until the patient is able to resume DUOPA infusion, if the patient will have prolonged interruption of therapy lasting more than 2 hours [see Dosage and Administration (2.4)].

Gastrointestinal and Gastrointestinal Procedure-Related Risks

Inform patients of the gastrointestinal procedure-related risks including abscess, bezoar, ileus, implant site erosion/ulcer, intestinal hemorrhage, intestinal ischemia, intestinal obstruction, intestinal perforation, intussusception, pancreatitis, peritonitis, pneumonia (including aspiration pneumonia), pneumoperitoneum, post-operative wound infection and sepsis. Advise patients of the symptoms of the above listed complications and instruct them to contact their healthcare provider if they experience any of these symptoms [see Warnings and Precautions (5.1)].

Falling Asleep during Activities of Daily Living and Somnolence

Alert patients to the potential sedating effects caused by DUOPA, including somnolence and the possibility of falling asleep while engaged in activities of daily living. Because somnolence is a common adverse reaction with potentially serious consequences, patients should not drive a car, operate machinery, or engage in other potentially dangerous activities until they have gained sufficient experience with DUOPA to gauge whether or not it affects their mental and/or motor performance adversely. Advise patients that if increased somnolence or episodes of falling asleep during activities of daily living (e.g., conversations, eating, driving a motor vehicle, etc.) are experienced at any time during treatment, they should not drive or participate in potentially dangerous activities until they have contacted their physician.

Advise patients of possible additive effects when patients are taking other sedating medications, alcohol, or other central nervous system depressants (e.g., benzodiazepines, antipsychotics, antidepressants, etc.) in combination with DUOPA or when taking a concomitant medication that increases plasma levels of levodopa [see Warnings and Precautions (5.2)].

Orthostatic Hypotension

Advise patients that they may experience syncope and may develop hypotension with or without symptoms such as dizziness, nausea, syncope, and sometimes sweating while taking DUOPA. Accordingly, caution patients against standing rapidly after sitting or lying down, especially if they have been doing so for prolonged periods and especially at the initiation of treatment with DUOPA [see Warnings and Precautions (5.3)].

Hallucinations/Psychosis/Confusion

Inform patients that they may experience hallucinations (unreal visions, sounds, or sensations) and other symptoms of psychosis can occur while taking DUOPA. Tell patients to report hallucinations, abnormal thinking, psychotic behavior or confusion to their healthcare provider promptly should they develop [see Warnings and Precautions (5.4)].

Impulse Control/Compulsive Behaviors

Advise patients that they may experience impulse control and/or compulsive behaviors while taking DUOPA. Advise patients to inform their physician or healthcare provider if they develop new or increased gambling urges, sexual urges, uncontrolled spending, binge or compulsive eating, or other urges while being treated with DUOPA [see Warnings and Precautions (5.5)].

Depression and Suicidality

Inform patients that they may develop depression or experience worsening of depression while taking DUOPA. Instruct patients to contact their healthcare provider if they experience depression, worsening of depression, or suicidal thoughts [see Warnings and Precautions (5.6)].

Withdrawal-Emergent Hyperpyrexia and Confusion

Advise patients to contact their healthcare provider before stopping DUOPA. Tell patients to inform their healthcare provider if they develop withdrawal symptoms such as fever, confusion, or severe muscle stiffness [see Warnings and Precautions (5.7)].

Dyskinesia

Inform patients that DUOPA may cause or exacerbate pre-existing dyskinesias [see Warnings and Precautions (5.8)].

Neuropathy

Inform patients that neuropathy may develop or they may experience worsening neuropathy on DUOPA, and to contact their healthcare provider if they develop any symptoms or features suggesting neuropathy [see Warnings and Precautions (5.9)].

Pregnancy

Advise patients to notify their healthcare provider if they become pregnant during treatment or plan to become pregnant during therapy [see Use in Specific Populations (8.1)].

Lactation

Advise patients to notify their healthcare provider if they are breastfeeding or plan to breastfeed [see Use in Specific Populations (8.2)].

Manufactured by AbbVie Inc., North Chicago, IL 60064, USA
or by HP Halden Pharma AS, Svinesundsveien 80, NO-1788 Halden, Norway
For AbbVie Inc.
North Chicago, IL 60064, USA

© 2025 AbbVie. All rights reserved. DUOPA and its design are trademarks of AbbVie AB.
20087899R2 Revised: 5/2025

MEDICATION GUIDE

DUOPA (Do-oh-pa)

(carbidopa and levodopa) enteral suspension

Read this Medication Guide before you start using DUOPA and each time you get a refill. There may be new information. This information does not take the place of talking to your healthcare provider about your medical condition or treatment.

What is the most important information I should know about DUOPA?

DUOPA can cause serious side effects, including:

- Stomach and intestine (gastrointestinal) problems and problems from the procedure you will need to have to receive DUOPA (gastrointestinal procedure-related problems).
  Some of these problems may require surgery and may lead to death.
  ○ a blockage of your stomach or intestines (bezoar)
  ○ stopping movement through intestines (ileus)
  ○ drainage, redness, swelling, pain, feeling of warmth around the small hole in your stomach wall (stoma)
  ○ bleeding from stomach ulcers or your intestines
  ○ inflammation of your pancreas (pancreatitis)
  ○ infection in your lungs (pneumonia)
  ○ air or gas in your abdominal cavity
  ○ skin infection around the intestinal tube, pocket of infection (abscess), infection in your blood (sepsis) or abdominal cavity may occur, after surgery
  ○ stomach pain, nausea or vomiting
- Tell your healthcare provider right away if you have any of the following symptoms of stomach and intestine problems and gastrointestinal procedure-related problems:
  ○ stomach (abdominal) pain
  ○ constipation that does not go away
  ○ nausea or vomiting
  ○ fever
  ○ blood in your stool or a dark tarry stool (melanotic stool)

You will need to have a procedure to make a small hole (called a “stoma”) in your stomach wall to place a gastro-jejunostomy tube (called a PEG-J tube) in an area of your small intestine called the jejunum. DUOPA is delivered directly to your small intestine through this tube. Your healthcare provider will talk to you about the stoma procedure. Before the stoma procedure, tell your healthcare provider if you have ever had a surgery or problems with your stomach.

Talk to your healthcare provider about what you need to do to care for your stoma. After the procedure, you and your healthcare provider will need to regularly check the stoma for any signs of infection.

If your PEG-J tube becomes kinked, knotted, or blocked this may cause you to have worsening of your Parkinson’s symptoms or recurring movement problems (motor fluctuations). Call your healthcare provider if your Parkinson’s symptoms get worse or you have slow movement while you are treated with DUOPA.

What is DUOPA?

DUOPA is a prescription medicine used for treatment of advanced Parkinson's disease. DUOPA contains 2 medicines, carbidopa and levodopa.

DUOPA should not be given to children (younger than 18 years).

Who should not use DUOPA?

Do not use DUOPA if you:

- take a medicine called a nonselective Monoamine Oxidase (MAO) Inhibitor (such as phenelzine or tranylcypromine) or have taken a nonselective MAO Inhibitor within the last 14 days.
  Ask your healthcare provider or pharmacist if you are not sure if you take an MAO Inhibitor.

What should I tell my healthcare provider before using DUOPA?

Before you use DUOPA, tell your healthcare provider if you:

- have or have had stomach ulcers or stomach surgery
- have low blood pressure (hypotension) or if you feel dizzy or faint, especially when getting up from sitting or lying down
- have had problems with fainting (syncope)
- feel sleepy or have fallen asleep suddenly during the day
- have or have had depression (feelings of hopelessness or sadness) or any mental problems
- drink alcohol. Alcohol can increase the chance that DUOPA will make you feel sleepy or fall asleep when you should be awake
- have trouble controlling your muscles (dyskinesia)
- have nerve problems (peripheral neuropathy)
- have or have had heart problems, an abnormal heart rate or have had a heart attack in the past
- have or have had high blood pressure (hypertension)
- have eye problems that cause increased pressure in your eye (glaucoma)
- have a history of attacks of suddenly falling asleep and without warning
- have any other medical conditions
- are pregnant or planning to become pregnant. It is not known if DUOPA will harm your unborn baby
- are breastfeeding or plan to breastfeed. DUOPA can pass into your milk and may harm your baby. Talk to your healthcare provider about the best way to feed your baby if you take DUOPA

Tell your healthcare provider about all the medicines you take, including prescription and over-the-counter medicines, vitamins, herbal supplements.

Using DUOPA with certain other medicines may affect each other and cause serious side effects.

Especially tell your healthcare provider if you take:

- medicines used to treat high blood pressure (hypertension)
- medicines used to treat depression called nonselective Monoamine Oxidase (MAO) Inhibitor (such as phenelzine or tranylcypromine) or have taken one within the last 14 days
- dopamine D2 receptor antagonists (antipsychotics or metoclopramide), and isoniazid
- iron or multivitamins with iron

Eating high protein foods may affect how DUOPA works. Tell your healthcare provider if you change your diet.

Ask your healthcare provider or pharmacist for a list of these medicines or foods if you are not sure.

Know the medicines you take. Keep a list of them to show your healthcare provider and pharmacist when you get a new medicine.

How should I use DUOPA?

- Use DUOPA exactly as your healthcare provider tells you to use it.
- Your healthcare provider should show you how to use DUOPA before you use it for the first time. Ask your healthcare provider or pharmacist if you have any questions.
- Your prescribed dose of DUOPA will be programmed into your pump by a healthcare provider and should only be changed by your healthcare provider or while you are with your healthcare provider.
- Do not stop using DUOPA or change your dose unless you are told to do so by your healthcare provider. Tell your healthcare provider if you develop withdrawal symptoms such as fever, confusion, or severe muscle stiffness.
- Keep a supply of oral carbidopa-levodopa immediate release (IR) tablets with you in case you are unable to give your DUOPA infusion.
- DUOPA is given continuously over 16 hours through a tube that is put into your stomach called a PEG-J. A small pump (CADD-Legacy 1400) is used to move DUOPA from the medication cassette through your PEG-J tube.
- Your DUOPA dose has three parts:
  ○ a morning dose
  ○ a continuous dose
  ○ extra doses
- DUOPA can also be given for a short time (short-term) through a tube put into your nose called a naso-jejunal (NJ) tube.
- The CADD-Legacy 1400 portable infusion pump should be used to give DUOPA through your PEG-J tube. See the Instructions for Use that comes with your CADD-Legacy 1400 portable infusion pump for complete instructions on how to use the pump.
- DUOPA comes in a small plastic container (cassette) that you connect to the pump to get your medicine.
  ○ Each cassette can only be used 1 time. An opened cassette should not be reused.
  ○ The cassette should not be used for longer than 16 hours.
  ○ The cassette should be thrown away at the end of the infusion, even if there is some medicine still in the cassette.
- Disconnect the pump from your PEG-J tube after the 16 hour dosing time is finished. Use a syringe filled with room temperature water to flush your PEG-J tube. See the “Instructions for Use” for more information about how to flush your PEG-J tube with a syringe.
- After your daily DUOPA infusion, you should take your usual night-time dose of oral carbidopa-levodopa tablets as prescribed.
- If you stop your DUOPA infusion for more than 2 hours during your 16 hour dosing time for any reason, call your healthcare provider and take oral carbidopa-levodopa as prescribed until you are able to restart your DUOPA infusion.
- If you stop your DUOPA infusion for less than 2 hours, you do not need to take oral carbidopa-levodopa, but your healthcare provider may tell you to take an extra dose of DUOPA.

What should I avoid while using DUOPA?

- Do not drive, operate machinery, or do other activities until you know how DUOPA affects you. Sleepiness and falling asleep suddenly caused by DUOPA can happen as late as 1 year after you start your treatment.

What are the possible side effects of DUOPA?

DUOPA may cause serious side effects, including:

- See “What is the most important information I should know about DUOPA?”
- Falling asleep during normal daily activities. DUOPA may cause you to fall asleep while you are doing daily activities such as driving, talking with other people, or eating.
  ○ You could fall asleep without any warning.
  ○ Some people using DUOPA have had car accidents because they fell asleep while driving.
  Do not drive or operate machinery until you are sure how DUOPA affects you.
  Tell your healthcare provider if you take other medicines that can make you sleepy such as sleep medicines, antidepressants, or antipsychotics.
- Low blood pressure when you sit or stand up quickly. After you have been sitting or lying down, stand up slowly until you know how DUOPA affects you. This may help reduce the following symptoms while you are using DUOPA:
  ○ dizziness
  ○ nausea
  ○ sweating
  ○ fainting
- Seeing things that are not there, hearing sounds or feeling sensations that are not real (hallucinations). Hallucinations can happen in people who use DUOPA. Tell your healthcare provider if you have hallucinations.
- Unusual urges. Some people taking certain medicines to treat Parkinson’s disease, including DUOPA, have reported problems, such as gambling, compulsive eating, compulsive shopping, and increased sex drive.
  If you or your family members notice that you are having unusual urges or behaviors, talk to your healthcare provider.
- Depression and suicide. DUOPA can cause depression or make your depression worse. Pay close attention to sudden changes in your mood, behavior, thoughts, or feelings. Call your healthcare provider right away if you feel depressed or have thoughts of suicide.
- Uncontrolled sudden movements (dyskinesia). If you have new dyskinesia, or your dyskinesia gets worse, tell your healthcare provider. This may be a sign that your dose of DUOPA or other medicines to control your Parkinson’s disease may need to be adjusted.
- Progressive weakness or numbness or loss of sensation in the fingers or feet (neuropathy).
- Heart attack or other heart problems. Tell your healthcare provider if you have experienced increased blood pressure, a fast or irregular heartbeat or chest pain.
- Abnormal blood tests. DUOPA may cause changes in certain blood tests, especially certain hormone and kidney function blood tests.
- Worsening of the increased pressure in your eyes (glaucoma). The pressure in your eyes should be checked after starting DUOPA.
- The most common side effects of DUOPA include:
  ○ swelling of legs and feet
  ○ nausea
  ○ high blood pressure (hypertension)
  ○ depression
  ○ mouth and throat pain

Call your healthcare provider or get medical care right away if you have any of the above symptoms. Your healthcare provider will tell you if you should stop treatment with DUOPA and if needed, tell you how to discontinue DUOPA.

Tell your healthcare provider if you have any side effect that bothers you or does not go away.

These are not all of the possible side effects of DUOPA. For more information, ask your healthcare provider or pharmacist.

Call your doctor for medical advice about side effects. You may report side effects to FDA at 1-800-FDA-1088.

How should I store DUOPA?

- Store DUOPA in the refrigerator between 36ºF to 46ºF (2ºC to 8ºC). Do not freeze.
- Use at room temperature. Take one DUOPA cassette out of the carton and out of the refrigerator 20 minutes prior to use. Use the product at room temperature or you may not get the right amount of medication.
- Protect the cassette from light and keep it in the carton before using.
- Use DUOPA before the expiration date printed on the cassette.

Keep DUOPA and all medicines out of the reach of children.

General information about the safe and effective use of DUOPA.

Medicines are sometimes prescribed for purposes other than those listed in a Medication Guide. Do not use DUOPA for a condition for which it was not prescribed. Do not give DUOPA to other people, even if they have the same symptoms that you have. It may harm them.

This Medication Guide summarizes the most important information about DUOPA. If you would like more information, talk with your healthcare provider. You can ask your healthcare provider or pharmacist for information about DUOPA that was written for healthcare professionals.

For more information go to www.DUOPA.com or call 1-844-386-4968.

What are the ingredients in DUOPA?

Active ingredients: carbidopa and levodopa

Inactive ingredients: carmellose sodium and purified water

This Medication Guide has been approved by the U.S. Food and Drug Administration.

Manufactured by AbbVie Inc., North Chicago, IL 60064, USA
or by HP Halden Pharma AS, Svinesundsveien 80, NO-1788 Halden, Norway
For AbbVie Inc.
North Chicago, IL 60064, USA

© 2025 AbbVie. All rights reserved. DUOPA and its design are trademarks of AbbVie AB.
20087899R2 Revised: 5/2025

INSTRUCTIONS FOR USE

DUOPA
(carbidopa and levodopa) enteral suspension
These instructions are for use along with any other instructions your healthcare provider gives you.
Please read the Medication Guide before you start using DUOPA and each time you get a refill.
For questions or problems, call DUOPA support toll free at 1-844-386-4968.

The CADD-Legacy® 1400 pump is used for delivery of DUOPA through a tube into your stomach attached to the longer straight (green) connector. Enteral nutrition should only be given by the shorter angled connector (white, blue, or violet) (see Figure A and Table. Connector Colors).

Table. Connector Colors.
Y-Connector Size | Design | Gastric (“g”) Port Color | Intestinal (“i”) Port Color
15 FR | Original | White
 | New | Blue | Green
20 FR | Original | White
 | New | Violet

Note: The original design of the Y-Connector is represented in the Figures throughout this Instructions for Use.
This Instructions for Use provides information for the CADD-Legacy® model 1400 pump only. There are other CADD-Legacy® pump models available. Read the label on the back of the pump to make sure it is a model 1400 pump.
Your healthcare provider prescribed DUOPA for you. Your healthcare provider programs your prescription into the CADD-Legacy® 1400 pump. The CADD-Legacy® 1400 pump is approved for use with DUOPA. DUOPA is provided as medication inside cassettes that connect to the CADD-Legacy® 1400 pump.

The pump delivers DUOPA in 3 ways:

- Continuous Rate: Steady delivery of DUOPA delivered throughout the day while pump is on
- Morning Dose: A large dose of DUOPA given each morning
- Extra Dose: A small dose of DUOPA given as needed during the day

You will need the following items to complete these steps:

- Pump
- DUOPA cassette
- Coin, like a quarter
- Carrying bag
- Syringe
- Syringe connector
- Room temperature water

CADD-Legacy®-1400 Pump

Display
The display shows programming information and messages. The main screen, which the pump displays most of the time, shows the following:

DUOPA Cassette
The single-use DUOPA cassette is for use with the CADD-Legacy® 1400 pump.
Battery Compartment
Two AA batteries fit into the battery compartment.
Cassette Latch
The cassette latch secures the DUOPA cassette to the pump.

WARNINGS and CAUTIONS

Failure to follow the Warnings and Cautions below could cause return of your symptoms, damage to the pump, serious injury, or may lead to death in rare cases.

WARNINGS

- Only use the pump in a manner described in this Instructions for Use, after you have received training by your healthcare provider.
- To avoid explosion hazard, do not use the pump near flammable explosive gases.
- Only use extension sets that are approved for use with DUOPA (See the Full Prescribing Information for DUOPA), pay attention to all warnings and cautions associated with their use.
- Always have new batteries available for replacement. If power is lost, DUOPA will not be delivered.
- If the pump is dropped or hit, the battery door or tabs may break. Do not use the pump if the battery door or tabs are damaged because the batteries will not be correctly secured. This may cause loss of power and DUOPA will not be delivered.
- If the pump is dropped or hit, look at the pump for damage. Do not use a pump that is damaged or is not functioning correctly.
- If a gap is present between the battery door and the pump housing, this means the door is not correctly latched. If the battery door becomes detached or loose, the batteries will not be correctly secured. This could cause loss of power and DUOPA will not be delivered.
- Use only DUOPA cassettes for pump accuracy and to make sure the pump works correctly. Attach the DUOPA cassette correctly. A detached or incorrectly attached DUOPA cassette could cause a problem with getting your DUOPA.

CAUTIONS

- Use only Smiths Medical accessories and replacement parts for the pump as using other brands may adversely affect the operation of the pump.
- Do not operate the pump at temperatures below 36°F (2°C) or above 104°F (40°C).
- Do not store the pump at temperatures below -4°F (-20°C) or above 140°F (60°C). Do not store the pump with a DUOPA cassette attached. Use the protective cassette provided when storing the pump.
- Do not keep the pump in humidity levels below 20% or above 90% relative humidity.
- Do not place the pump in cleaning fluid or water, or allow solution to soak into the pump, keypad, or battery compartment.
- Do not clean the pump with acetone, other plastic solvents, or abrasive cleaners.
- Do not use rechargeable NiCd or nickel metal hydride (NiMH) batteries. Do not use carbon zinc (heavy duty) batteries. They do not provide enough power for the pump to operate correctly.
- Do not store the pump for long periods of time with the batteries installed. Battery leakage could damage the pump.

Morning Procedure

- Take the DUOPA carton containing the DUOPA cassettes out of the refrigerator. Check the expiration date on the carton. Do not use any of the cassettes if the expiration date has passed.
- Take a DUOPA cassette out of the carton. Return the carton with the remaining cassettes to the refrigerator. Do not use the cassette if the expiration date has passed or the cassette is damaged or empty. Leave the DUOPA cassette at room temperature for 20 minutes before using.
- Each DUOPA cassette may be used for up to 16 hours after removal from the refrigerator.

WARNING: Use only DUOPA cassettes to make sure the pump works correctly.

1) Remove the cassette clip (see Figure B):

- Remove the cassette tube from its slot in the clip.
- Pull the clip from cassette to slide it off of the cassette top.

2) Attach the DUOPA cassette to the pump (see Figure C):

- Hold the pump so the latch faces up.
- Hold the DUOPA cassette so the tube points down.
- Insert the DUOPA cassette hooks into the hinge pins at the base of the pump.

3) Latch the DUOPA cassette into the pump:

- Hold the pump and DUOPA cassette upright against a flat surface.
- Press down on the pump, until the DUOPA cassette fits tightly against the pump (see Figure D).
- Use a coin to twist the latch counterclockwise until the latch lines up straight with the arrow (see Figure E).

WARNING: Attach the DUOPA cassette correctly. A detached or incorrectly attached cassette could cause a problem with getting your DUOPA.

4) Remove the red cap on the end of the cassette tube (see Figure F). Save the red cap for use when you throw away the cassette.
WARNING: Do not connect the red cap to the stomach tube. It will block DUOPA flow.

5) Connect the stomach tube to the cassette tube:

- While holding the stomach tube steady, twist off the white cap on the end of the longer straight (green) connector (see Figure G). WARNING: Do not twist the stomach tube.
- Connect the cassette tube to the end of the longer straight (green) connector (see Figure H). Do not connect to the shorter angled connector (white, blue, or violet).

6) Turn the pump on:

- Press and hold

until the display turns on.

- Wait approximately 30 seconds for the pump to review settings.
- Check for

on the screen.
PUMP STATUS: The pump is now on but not yet delivering DUOPA.

7) Inspect the tubing for kinks or closed clamps. If needed straighten kinks or open clamps (see Figure I).

8) Start the pump:

- Press and hold

until 3 dashes appear and then disappear from the screen.

- Wait approximately 15 seconds for the pump to start running.
- Check for

on the display.

PUMP STATUS: The pump is now running. DUOPA delivery will begin as programmed by your healthcare provider. If the pump will not start, a message should appear on the display. Refer to the Alarms and Messages section.

It will take between 10 minutes and 30 minutes to deliver your morning dose. To start delivery of your Morning Dose you will need to press the Morning Dose key 2 times.
NOTE: If you are unable to deliver your Morning Dose, it may be too soon since the last Morning Dose to deliver another dose. You may need to wait longer. The time between Morning Doses is decided by your healthcare provider.

9) The first key press shows the Morning Dose on the display.

- Press

- Check for

on the display. The number on your display is the Morning Dose of DUOPA your healthcare provider prescribed for you.

10) The second key press starts Morning Dose delivery.

- Press

a second time to deliver the Morning Dose.

- The display

shows a countdown of your Morning Dose.

PUMP STATUS: After the Morning Dose finishes, the pump will automatically begin delivering the Continuous Rate. RUN will appear on the display. This completes DUOPA delivery for your Morning Procedure.

11) Insert pump into the carrying bag (see Figure J).

- Other carrying cases are also available. Refer to the specific Instructions for Use, which accompanies your carrying case.

12) Wear the bag over your shoulder or neck:

- Place the bag strap over your shoulder or neck (see Figure K).
- Make sure the pump is in correct position (see Figure L).

Extra Dose

1) Give an Extra Dose of DUOPA:
NOTE: If you are unable to deliver the Extra Dose, it may be too soon since the last Extra Dose to deliver another and you may need to wait longer. The time between Extra Doses and the amount of DUOPA in the Extra Dose is decided by your healthcare provider.

- Check for

on the display.

- Press

- Listen for 2 beeps.
- The display will show

PUMP STATUS: The pump is now delivering the Extra Dose. When it finishes, RUN will appear on the display and the Continuous Rate will continue to run.

For instructions on changing a DUOPA cassette, see Changing the Cassette.

Evening Procedure

You will need:

- 1 Syringe
- 1 Syringe connector
- Room temperature water
- 1 Coin, like a quarter

1) Remove the pump from the carrying bag (see Figure M).

2) Stop the Continuous Rate:

- Press and hold

until 3 dashes appear and then disappear from the display.

- Check for

on the display.

3) Turn the pump off:

- Press and hold

until 3 sets of dots appear and then disappear from the display and the display turns off.

- Check that the display is off.

4) Clamp the cassette tube (see Figure N).

5) Disconnect the tubing:

- Twist the cassette tube to disconnect it from the longer straight (green) connector (see Figure O). WARNING: Do not twist the stomach tube.
- Replace the red cap on the cassette tube.

6) Flush the longer straight (green) connector:

- Connect the syringe connector to the longer straight (green) connector.
- Fill a syringe with room temperature tap or drinking water. Do not use hot water as it could burn the wall of your stomach or intestine.
- Connect the syringe to the syringe connector (see Figure P). Do not over-tighten the syringe connector or it could break. Do not use the syringe connector if it is cracked or broken.
- Push the syringe plunger to flush the tube. Do not force the syringe if flushing the tube is difficult. Call your healthcare provider if you are unable or have difficulty flushing your tube.
- Remove the syringe and the syringe connector.
- Replace the white cap on the longer straight (green) connector (see Figure Q).

7) Flush the shorter angled connector (white, blue, or violet):

- Twist the white cap off the shorter angled connector (white, blue, or violet).
- Connect the syringe connector to the shorter angled connector (white, blue, or violet).
- Fill a syringe with room temperature tap or drinking water. Do not use hot water as it could burn the wall of your stomach or intestine.
- Connect the syringe to the syringe connector (see Figure R). Do not over-tighten the syringe connector or it could break. Do not use the syringe connector if cracked or broken.
- Push the syringe plunger to flush the tube.
- Remove the syringe and the syringe connector.
  Replace the white cap on the shorter angled connector (white, blue, or violet) (see Figure S).

8) Remove the DUOPA cassette from the pump:

- Hold the pump and DUOPA cassette upright against a flat surface (see Figure T).
- Use a coin to twist the latch clockwise until the latch pops out (see Figure U).
- Remove the DUOPA cassette from the pump.

Changing the DUOPA Cassette

- Take the DUOPA carton containing the DUOPA cassette out of the refrigerator. Check the expiration date on the carton. Do not use any of the cassettes if the expiration date has passed.
- Take a DUOPA cassette out of the carton. Return the carton with the remaining cassettes to the refrigerator. Do not use the cassette if the expiration date has passed or the cassette is damaged or empty. Leave the DUOPA cassette at room temperature for 20 minutes before using.
- Each DUOPA cassette may be used for up to 16 hours after removal from the refrigerator.

WARNING: Use only DUOPA cassettes to make sure the pump works correctly.

1) Remove the pump from the carrying bag (see Figure V).

2) Stop the Continuous Rate:

- Press and hold

until 3 dashes appear and then disappear from the display.

- Check for

on the display.

3) Turn the pump off:

- Press and hold

until 3 sets of dots appear and then disappear from the display and the display turns off.

- Check that the display is off.

4) Clamp the cassette tube (see Figure W).

5) Disconnect the tubing:

- Twist the cassette tube to disconnect it from the longer straight (green) connector (see Figure X). WARNING: Do not twist the stomach tube.
- Replace the red cap on the cassette tube.

6) Remove the DUOPA cassette from the pump:

- Hold the pump and DUOPA cassette upright against a flat surface (see Figure Y).
- Use a coin to twist the latch clockwise until the latch pops out (see Figure Z).
- Remove the DUOPA cassette from the pump.

7) Remove the cassette clip on the new DUOPA cassette (see Figure AA):

- Remove the cassette tube from its secured slot in the clip.
- Pull the clip from the cassette to slide it off of the cassette top.

8) Attach the new DUOPA cassette to the pump (see Figure BB):

- Hold the pump so that the latch faces up.
- Hold the DUOPA cassette so that the tube points down.
- Insert the DUOPA cassette hooks into the hinge pins at the base of the pump.

9) Latch the new DUOPA cassette into the pump:

- Hold the pump and DUOPA cassette upright against a flat surface.
- Press down on the pump until the DUOPA cassette fits tightly against the pump (see Figure CC).
- Use a coin to twist the latch counterclockwise until the latch lines up straight with the arrow (see Figure DD).

WARNING: Attach the DUOPA cassette correctly. A detached or incorrectly attached cassette could cause a problem with getting your DUOPA.

10) Remove the red cap on the end of the cassette tube (see Figure EE).
Save the red cap to use when discarding the cassette.
WARNING: Do not connect the red cap to the stomach tube as it will block DUOPA flow.

11) Connect the stomach tube to the cassette tube:

- While holding the stomach tube steady, twist off the white cap on the end of the longer straight (green) connector (see Figure FF). WARNING: Do not twist the stomach tube.
- Connect the cassette tube to the end of the longer straight (green) connector (see Figure GG). Do not connect to the shorter angled connector (white, blue, or violet).

12) Turn the pump on:

- Press and hold

until the display turns on.

- Wait approximately 30 seconds for the pump to review settings.
- Check for

on the display.
PUMP STATUS: The pump is now on but not delivering DUOPA.

13) Inspect the tubing for kinks or closed clamps. If needed straighten kinks or open clamps (see Figure HH).

14) Start the pump:

- Press and hold

until 3 dashes appear and then disappear from the display.

- Wait approximately 15 seconds for pump to start running.
- Check for

on the display.
PUMP STATUS: The pump is now running.

15) Insert the pump into the carrying bag (See Figure II).

16) Wear the bag on your shoulder or neck:

- Place the bag strap over your shoulder or neck (see Figure JJ).
- Make sure the pump is in correct position (see Figure KK).

Changing the Batteries:
If you see LowBat or Battery Depleted on the display, change the batteries. Use 2 new AA alkaline batteries such as DURACELL® or EVEREADY® ENERGIZER®. The pump keeps all the important information when the batteries are removed.
WARNING:

- Always have new batteries available for replacement. If power is lost, DUOPA will not be delivered.
- If the pump is dropped or hit, the battery door or tabs may break. Do not use the pump if the battery door or tabs are damaged because the batteries will not be correctly secured. This may lead to loss of power and DUOPA will not be delivered.
- If a gap is present anywhere between the battery door and the pump housing, the door is not correctly latched. If the battery door becomes detached or loose, the batteries will not be correctly secured. This could cause loss of power and DUOPA will not be delivered.

CAUTION:

- Do not use rechargeable NiCd or nickel metal hydride (NiMH) batteries. Do not use carbon zinc (“heavy duty”) batteries. They do not provide enough power for the pump to operate correctly.
- Do not store the pump for prolonged periods of time with the batteries installed. Battery leakage could damage the pump.

1) Ensure the pump is stopped.

2) Push and hold the arrow button while sliding the battery door until it comes completely off the pump (see Figure LL).

3) Remove the used batteries (see Figure MM).

4) Install new batteries into the battery compartment.
NOTE: Insert the batteries correctly based on the picture in the battery compartment. If you insert the batteries backwards, the display will remain blank. Reinsert the batteries, making sure to match the + and – markings with the battery compartment picture.

5) Listen for a beep.
PUMP STATUS: The pump is now powered. The power-up sequence will start, the pump will go through an electronic self-test, and then the pump will beep 6 times at the end of the power-up sequence. All of the display indicators, the software revision, and each setting will appear briefly.
If you do not hear a beep, and the display is off, the pump is not powered. Check that the batteries are correctly inserted.

6) Slide the battery door back onto the pump into its original closed position (see Figure NN).

Change the Morning Dose

Your healthcare provider may have set your pump to allow for dose changes to your Morning Dose and Continuous Rate (Lock Level 1). Do not change your medicine dose without approval and training from your healthcare provider.
Talk with your healthcare provider to decide when to change your Morning Dose and Continuous Rate. Do not change your Extra Dose unless your healthcare provider tells you to. If your Extra Dose requires changes, your healthcare provider will provide instructions.

Change the Morning Dose

WARNING: Do not use the Prime button. Priming is for use by your healthcare provider only.

1) Turn the pump on:

- Press and hold

until the display turns on.

- Wait approximately 30 seconds for pump to review settings.
- Check for

on the display.
PUMP STATUS: The pump is now on but not yet delivering DUOPA.

2) Inspect the tubing for kinks or closed clamps. If needed, straighten kinks or open clamps (see Figure OO).

3) Start the pump:

- Press and hold

until 3 dashes appear and then disappear from the display.

- Wait approximately 15 seconds for pump to start running.
- Check for

on the display.
PUMP STATUS: The pump is now running.

4) Change the Morning Dose:
a. Press

1. time.

b. Check for
on the display.
c. Press
or
to select the desired Morning Dose.
d. Press
to store the Morning Dose.
e. Make sure you see the correct Morning Dose on the display. If not, repeat Steps 4c to 4e.

5) Deliver the Morning Dose:

- Press

1 time.
NOTE: If you see “Value not saved” on the display, press NEXT and then repeat Steps 4c to 4e.

- The display

shows a countdown of your Morning Dose.
PUMP STATUS: After the Morning Dose finishes, the pump will begin delivering the Continuous Rate. RUN will appear on the display.
NOTE: If you are unable to deliver a Morning Dose, it may be too soon since the last Morning Dose to deliver another and you may need to wait longer. The time between Morning Doses is decided by your healthcare provider.

Change the Continuous Rate

1) Stop the Continuous Rate:

- Press and hold

until 3 dashes appear and then disappear from the display.

- Check for

on the display.

2) Change the Continuous Rate:
a. Press
2 times.
b. Check for
on the display.
c. Press
or
to select the desired Continuous Rate.
d. Press
to store the Continuous Rate.
e. Make sure you see the desired Continuous Rate on the display. If not, repeat Steps 2c to 2e.

3) Start the pump:

- Press and hold

until 3 dashes appear and then disappear from the display.
NOTE: If you see “Value not saved” on the display, press NEXT and then repeat Steps 2c to 2e.

- Wait approximately 15 seconds for the pump to start running.
- The display will show

PUMP STATUS: The pump is now running.

Alarms and Messages
The table below shows some of the common alarms that you may hear from the pump. With all alarms, read the display before pressing
to silence the alarm.
What you see: | What you hear: | Meaning | Response
Error | Two-Tone Alarm | An error with the pump has occurred. | Contact your healthcare provider.
High Pressure | Two-Tone Alarm | There is pressure backed up in the tubing. | Check tubing for clamps, kinks, or blockages. Make sure the red cap has been removed from the DUOPA cassette tube. Flush connectors if necessary. If it is not possible to flush the tubes, contact your healthcare provider as your tube may be blocked.
LowBat | 3 Two-Tone Beeps Every 5 minutes | The pump batteries are low. | Change the batteries right away.
Upstream Occlusion | Two-Tone Alarm | If your healthcare provider has the Upstream Occlusion Sensor set to ON and a blockage in the DUOPA cassette is detected, this alarm will sound. | Detach the DUOPA cassette. Check if the DUOPA cassette is empty. If not empty, reattach the DUOPA cassette. Restart the pump to continue delivery. Contact your healthcare provider if the alarm continues.
No message on display | Two-Tone Alarm | Batteries were removed within approximately 15 seconds after stopping the pump. | Install new batteries to silence the alarm. Otherwise, the alarm will stop within a short period of time.
Display shows current pump status | 2 Beeps (Long-Short) | The DUOPA cassette is not lined up with the pump or DUOPA is not flowing from the DUOPA cassette to the pumping mechanism. Very cold or extremely thick DUOPA may cause this alarm as well. | Press NEXT to silence the alarm. The pump continues to run. Make sure the DUOPA cassette is correctly lined up with the pump and DUOPA is flowing. Take the DUOPA cassette out of the refrigerator for 20 minutes before attaching to the pump.
Battery Depleted | Two-Tone Alarm | Batteries are dead. | Install new batteries. To continue delivery, restart the pump when completed.
Key pressed, Please release | Two-Tone Alarm | Key is being held down. | Stop pressing key. If the alarm persists, close the cassette tube clamp and remove the pump from use. Contact your healthcare provider.
No Disposable, Clamp Tubing | Two-Tone Alarm | Disposable refers to the DUOPA Cassette. No Disposable means the DUOPA cassette was removed. The pump is not sensing proper cassette attachment. | Clamp the cassette tube and disconnect it from your stomach tube. A DUOPA cassette must be correctly attached in order for the pump to run. Press NEXT to silence the alarm.
No Disposable, Pump won't run | Two-Tone Alarm | Disposable refers to the DUOPA Cassette. You have tried to start the pump without a disposable DUOPA cassette attached. | Press NEXT to silence the alarm. A DUOPA cassette must be correctly attached for the pump to run.
Service Due See manual | Two-Tone Alarm | The pump is scheduled for service. | Press NEXT to silence the alarm. The pump is still working, but contact your healthcare provider for further instructions.

Frequently Asked Questions

What if I drop the pump or hit it against a hard surface?
Do the following right away:

- Check the DUOPA cassette latch on the side of the pump and make sure the line on the latch lines up with the arrow on the side of the pump.
- Gently twist, push, and pull on the DUOPA cassette to make sure it is still firmly attached.
- Check the battery door to make sure it is still firmly attached.

If the DUOPA cassette or the battery door is loose or damaged, do not use the pump.
Stop the pump right away, close the tubing clamp, and contact your healthcare provider.

What should I do if I drop the pump in water?
If you accidentally drop the pump in water, pick it up quickly, dry it off with a towel, and call your healthcare provider.

WARNING: If the pump is dropped or hit, look at the pump for damage. Do not use a pump that is damaged or is not working correctly.

What should I do if I need to bathe while wearing the pump?
You’ll need to detach the pump before you shower, bathe, or swim. Reattach the pump to the stomach tubing afterwards and restart it.

What should I do if I need to have a medical test while wearing the pump?
The pump may need to be removed prior to certain medical tests. Be sure to talk to your doctor about your DUOPA pump before you take these tests.

STORAGE and DISPOSAL

Storage

- Store DUOPA in the refrigerator with the temperature between 36°F to 46°F (2°C to 8°C).
- When the DUOPA cassette has been removed from the refrigerator, DUOPA should be used within 16 hours.
- The DUOPA cassettes are for single use only and should not be used for longer than 16 hours, even if some of the medicine remains. An opened cassette should not be re-used.
- Protect the cassette from light and keep it in the carton before using.

Throwing away your DUOPA cassette or batteries

- Throw away the DUOPA cassette as your healthcare provider tells you to.
- Throw away used batteries in a manner safe for the environment, and according to any regulations that apply.

This Instructions for Use has been approved by the U.S. Food and Drug Administration.

AbbVie Inc.
North Chicago, IL 60064, U.S.A.
For DUOPA Support: 1-844-386-4968

Pump manufactured by:
Smiths Medical ASD, Inc.
1265 Grey Fox Road
St. Paul, MN 55112 USA
Tel: 1-800-258-5361
www.smiths-medical.com

03-B884 Revised: March 2019

Legacy 1400 Operator's Manual

CADD-Legacy® 1400 Pump
Model 1400

This online version differs from the printed version. Certain information that is not intended for patients has been removed.

This operator’s manual is for clinician use only. Read the entire operator’s manual before operating the pump.

This manual pertains only to the CADD-Legacy® 1400 pump. There are other CADD-Legacy® pump models available; review the rear label of the pump to ensure it is a CADD-Legacy® 1400 pump before programming. This pump is designed for enteral delivery of medication and can be programmed to deliver a continuous rate, a morning dose, and extra doses.

This manual is intended for clinician use only. Do not permit patients to have access to this manual. The pump has 3 security levels designed to limit patient access. Do not disclose the pump’s security codes or any other information that would allow inappropriate access to programming and operating functions.

The issue date of this operator’s manual is included on the back cover for the clinician’s information. In the event one year has elapsed between the issue date and product use, the clinician should contact Smiths Medical to see if a later revision of this manual is available.

Technical Assistance

If you have comments or questions concerning the operation of the CADD-Legacy® 1400 pump, please call the number given below. When calling, please specify the pump’s software revision. This information is located on the pump’s display during power up.

Our staff at Smiths Medical is available to help clinicians 24 hours a day with the programming and operation of the CADD-Legacy® 1400 pump.

Smiths Medical ASD, Inc.
1265 Grey Fox Road
St. Paul, MN 55112 USA
Tel: 1 800 258 5361 (USA)
Tel: +1 614 210 7300
www.smiths-medical.com

Read this entire operator’s manual before operating the CADD-Legacy® 1400 pump.

Failure to follow the warnings and cautions below could result in return of symptoms, damage to the pump, serious injury, or death in extreme cases.

Please refer to the full prescribing information for DUOPA (carbidopa and levodopa) enteral suspension for indications and usage, contraindications, warnings, precautions, and adverse reactions.

Warnings

- This operator’s manual should be used by clinicians only. Do not permit patients to have access to this manual, as the information contained would allow the patient complete access to all programming and operating functions. Improper programming could compromise patient treatment.
- To avoid explosion hazard, do not use the pump in the presence of flammable anesthetics or explosive gases.
- The CADD-Legacy® 1400 pump and medication cassette reservoir are designed for enteral delivery of medication only. They are NOT intended for IV or other parenteral routes of infusion.
- Do not disclose to the patient the pump’s security codes or any other information that would allow the patient complete access to all programming and operating functions. Improper programming could compromise patient treatment.
- Always have new batteries available for replacement. If power is lost, non-delivery of medication will occur.
- If the pump is dropped or hit, the battery door or tabs may break. Do not use the pump if the battery door or tabs are damaged because the batteries will not be properly secured; this may result in loss of power and non-delivery of medication.
- If a gap is present anywhere between the battery door and the pump housing, the door is not properly latched. If the battery door becomes detached or loose, the batteries will not be properly secured; this could result in loss of power and non-delivery of medication.
- System delivery inaccuracies beyond the stated accuracy may occur as a result of back pressure or fluid resistance, which depends upon temperature, medication viscosity, catheter size, extension set tubing, flow rate, and orientation of the pump system.
- Programming the pump at a delivery rate other than what is prescribed will cause over- or under-delivery of medication.
- Clamp the fluid path tubing and/or disconnect the tubing from the enteral access device before removing the medication cassette reservoir from the pump to prevent unintended delivery of medication.
- Use only approved DUOPA medication cassette reservoirs to maintain pump accuracy and assure proper pump operations.
- Use only extension sets approved for use with DUOPA, paying particular attention to all warnings and cautions associated with their use.
- Attach the cassette properly. The cassette is the part of the medication cassette reservoir that attaches to the pump. A detached or improperly attached cassette could result in unintended delivery of medication.
- Do not prime the fluid path with the tubing connected to a patient as this could result in over-delivery of medication.
- If the pump is dropped or hit, inspect the pump for damage. Do not use a pump that is damaged or is not functioning properly, as this could compromise patient treatment.
- The use of power supplies and a remote dose cord other than those listed in the electromagnetic emissions declaration may result in increased emissions or decreased immunity of the pump.
- The pump should not be used adjacent to or stacked with other equipment. If adjacent or stacked use is necessary, the user should verify normal operation of the pump in the configuration in which it is to be used.
- There are potential health hazards associated with improper disposal of batteries, electronics, and contaminated (used) reservoirs and extension sets. Dispose of used batteries, reservoirs, extension sets and other used accessories, or a pump that has reached the end of its useful life, in an environmentally safe manner, and according to any regulations that may apply.

Cautions

- Use only Smiths Medical accessories and replacement parts, as using other brands may adversely affect the operation of the pump.
- Do not operate the pump at temperatures below 2°C (36°F) or above 40°C (104°F).
- Do not store the pump at temperatures below -20°C (-4°F) or above 60°C (140°F). Do not store the pump with the medication cassette reservoir attached. Use the protective cassette provided.
- Do not expose the pump to humidity levels below 20% or above 90% relative humidity.
- Do not sterilize the pump or medication cassette reservoir as this could cause damage.
- When the upstream occlusion sensor is turned off, the pump will not detect occlusions in the medication cassette reservoir. Periodically inspect the medication cassette reservoir for decreasing volume. Undetected occlusions could result in under- or non-delivery of medication.
- Do not use rechargeable NiCd or nickel metal hydride (NiMH) batteries. Do not use carbon zinc (“heavy duty”) batteries. They do not provide sufficient power for the pump to operate properly.
- Do not store the pump for prolonged periods of time with the batteries installed. Battery leakage could damage the pump.
- Prior to starting medication delivery, inspect the fluid path for kinks, a closed clamp, or other obstruction. An undetected occlusion may result in under- or non-delivery of medication and/or nuisance alarms.
- When you enter a new value, any lockout time already in effect will be cleared. An extra dose or morning dose could be requested and delivered immediately upon starting the pump, which may result in over-delivery of medication.
- Do not immerse the pump in cleaning fluid or water. Do not allow solution to soak into the pump, accumulate on the keypad, or enter the battery compartment. Moisture buildup inside the pump may damage the pump.
- Do not clean the pump with acetone, other plastic solvents, or abrasive cleaners, as damage to the pump may occur.
- Do not expose the pump to therapeutic levels of ionizing radiation as permanent damage to the pump’s electronic circuitry may occur. The best procedure to follow is to remove the pump from the patient during therapeutic radiation sessions. If the pump must remain in the vicinity during a therapy session, it should be shielded, and its ability to function properly should be confirmed following treatment.
- Do not expose the pump directly to ultrasound, as permanent damage to the electronic circuitry may occur.
- Do not use the pump in the vicinity of magnetic resonance imaging (MRI) equipment as magnetic fields may adversely affect the operation of the pump. Remove the pump from the patient during MRI procedures and keep it at a safe distance from magnetic energy.
- This pump may interfere with ECG equipment. Monitor ECG equipment carefully when using this pump.
- CADD-Legacy® 1400 pumps are sealed units. A broken or damaged seal will, therefore, be considered conclusive evidence that the pump has been misused and/or altered, which voids any and all warranties. All service and repair of CADD-Legacy® 1400 pumps must be performed by Smiths Medical or its authorized agents.
- Review programming screens when complete to make sure desired programming has been entered. Check to make sure unintended changes were not made to the morning dose, continuous rate, or extra dose volume. If unintended changes were made, go to the appropriate screen and program the desired value.

Table of Contents

Warnings

Cautions

1.0 General Description

Introduction

Indications

Symbols

Pump Diagram

Description of the Keys, Display, and Features

The Main Screen

Lock Levels

Security Codes

Lock Level 0 (LL0) Table

Lock Levels 1 and 2 (LL1, LL2) Table

2.0 Pump Setup and Programming

Installing or Replacing the Batteries

Watching Power Up

Changing to Lock Level 0 (LL0)

Programming the Pump: General Instructions

Delivery Methods

Programming Screens

Programming Delivery

Programming a Morning Dose

Removing a Medication Cassette Reservoir

Attaching a Medication Cassette Reservoir

Priming the Tubing and Connecting to the Patient

Setting the Lock Level for the Patient

Programming with Upper Limits, Adjusting Doses in Lock Level 1

3.0 Operating the Pump

Starting the Pump

Stopping the Pump

Turning the Pump On/Off

Starting a Morning Dose

Starting an Extra Dose

Stopping an Extra Dose or Morning Dose

Resetting the Reservoir Volume

4.0 Biomed Functions

Overview: Accessing the Biomed Functions and Programming the Lockouts

Extra Dose Lockout

Morning Dose Lockout

Upstream Occlusion Sensor On/Off

5.0 Reference

Messages and Alarms, Alphabetical List

What if the pump is dropped or hit?

Cleaning the Pump and Accessories

Exposure to Radiation, Ultrasound, Magnetic Resonance Imaging (MRI), or Use near ECG Equipment

Continuous Rate Scroll Ranges

Extra Dose, Morning Dose Scroll Ranges

Technical Description

Specifications (Nominal)

Accuracy Test Results

Electromagnetic Emissions and Immunity Declarations

Safety Features and Fault Detection

Software Safety Features

Data Handling Software Safety Features

Annual Functional Inspection

Collect Separately

Limited Warranty

Index

Appendix A – Pump Programming Quick Reference for Healthcare Providers

1.0 General Description

Introduction

The CADD-Legacy® 1400 pump provides enteral delivery of medication to patients in hospital or outpatient settings. Therapy should always be overseen by a physician or a certified, licensed healthcare professional. As appropriate to the situation, the patient should be instructed in using and troubleshooting the pump.

Indications

The CADD-Legacy® 1400 pump is indicated solely for the enteral delivery of medication contained in a medication cassette reservoir supplied by AbbVie. The medication cassette reservoir attaches to the bottom of the pump.

WARNING: The CADD-Legacy® 1400 pump and medication cassette reservoir are designed for enteral delivery of medication only. They are NOT intended for IV or other parenteral routes of infusion. Use of this product for medications or therapies outside the intended use can result in death or serious patient injury.

Refer to AbbVie’s full prescribing information for DUOPA (carbidopa and levodopa) enteral suspension for indications and usage, contraindications, warnings, precautions, and adverse reactions.

Symbols

Direct current (power jack)

Accessory jack

Caution

Class II equipment

Type CF equipment

Splashproof – water splashed against the pump housing will have no harmful effects (see Cleaning the Pump and Accessories, Section 5, for additional important information).

Catalog number

Serial number

Date of manufacture

Manufacturer

CAUTION: Federal (USA) law restricts this device to sale by or on the order of a physician.

Collect separately

Temperature limitation

Humidity limitation

Atmospheric pressure limitation

MR Unsafe

Pump Diagram

Description of the Keys, Display, and Features

AC Indicator Light

The green indicator light is on when you are using the AC adapter to power the pump.

Display

The liquid crystal display (LCD) shows programming information and messages. In this manual, the term “display” is synonymous with display panel or LCD.

Keypad

The keys on the keypad are described below. A key beeps when pressed if it is operable in the current lock level.

used to start and stop pump delivery; silences alarms.

used to enter (save) a new value in the pump’s memory when programming doses or pump settings or to clear values from record-keeping screens. It is also used to return from the biomed functions to the main screen (see Section 4).

used to fill the tubing with medication.

used to confirm and deliver the morning dose (typically used as a daily loading dose) when the pump is running. When the pump is stopped, it is used to view or change the pump’s current lock level. Lock levels are used to limit patient access to certain programming and operating functions. (See Lock Levels, this section.)

used to move from one programming screen to the next without changing the setting or value displayed; silences alarms.

used to “scroll up” or increase a value, or scroll through biomed function settings.

used to “scroll down” or decrease a value, or scroll through biomed function settings.

used to put the pump into a low power state when not in use or back into full power.

used by the patient to deliver a programmed amount of medication upon request (extra dose).

Power Jack

You may plug an AC adapter into the power jack as an alternate source of power. The indicator light on the front of the pump will illuminate when the AC adapter is in use.

Accessory Jack

The accessory jack is used for attaching accessory cables. See the instructions for use supplied with those accessories.

Medication Cassette Reservoir

The medication cassette reservoir is the single-use reservoir designed for use with the CADD-Legacy® 1400 pump. In this manual and on the pump’s display, the word “disposable” refers to the medication cassette reservoir. In AbbVie’s patient instructions for use, medication cassette reservoir is referred to as DUOPA cassette.

Battery Compartment

Two AA batteries fit into the battery compartment. The AA batteries serve as the primary source of power, or as backup power when an AC adapter is in use.

Cassette Latch

The cassette latch attaches the cassette to the pump. The term “cassette” refers to the part of the medication cassette reservoir that attaches to the bottom of the pump. If the cassette becomes unlatched while the pump is running, delivery will stop and an alarm will occur. If the cassette becomes unlatched while the pump is stopped, an alarm will occur.

Other Features Not Shown

Upstream Occlusion Sensor: The pump contains an upstream occlusion sensor. This feature may be turned on or off (see Section 4, Biomed Functions). When the sensor is turned on, and an occlusion in the reservoir is detected, an alarm will sound, delivery will stop, and the display will show Upstream Occlusion.

CAUTION: When the upstream occlusion sensor is turned off, the pump will not detect occlusions in the medication cassette reservoir. Periodically inspect the medication cassette reservoir for decreasing volume. Undetected occlusions could result in under- or non-delivery of medication.

Downstream Occlusion Sensor: The pump contains a downstream occlusion sensor. When a downstream occlusion (between the pump and the patient) is detected, an alarm will sound, delivery will stop, and the display will show High Pressure.

Reservoir Volume Alarm: The reservoir volume alarm indicates when the volume of medication in the medication cassette reservoir is low or depleted. Each time you change the medication cassette reservoir, you may reset the reservoir volume to the originally programmed value. Then, as medication is delivered, the reservoir volume automatically decreases. When the pump calculates that 5 ml remain in the medication cassette reservoir, beeps sound and ResVol Low appears on the main screen. This alarm recurs at every subsequent decrease of 1 ml until the reservoir volume reaches 0 ml, at which point the pump stops and the reservoir volume empty alarm sounds.

NOTE: The default setting for Reservoir Volume is Not in Use. The reservoir volume alarm is activated only when a value is programmed into the Reservoir Volume screen. Programming a reservoir volume value is not required for general use, but is available at provider discretion.

The Main Screen

The main screen is the starting point for programming or viewing the pump’s settings.

If no keys are pressed for 2 minutes, the display reverts to the main screen. When the two AA batteries are low, LowBat appears on the main screen.

*Does not appear on the main screen if reservoir volume is programmed to Not In Use.

Lock Levels

Lock levels are used to limit patient access to certain programming and operating functions. The table on the next page lists the functions that are accessible in lock level 0 (LL0), lock level 1 (LL1), and lock level 2 (LL2). When a function is accessible, the key associated with the function beeps when pressed. If a function is not accessible, the pump ignores the key press and a beep does not sound. Section 2, Pump Setup and Programming, describes how to change the lock level.

Security Codes

The following security codes are preset by the manufacturer for the clinician’s use:

**Text Omitted**

WARNING: Do not disclose to the patient the pump’s security codes or any other information that would allow the patient complete access to all programming and operating functions. Improper programming could compromise patient treatment.

Lock Level 0 (LL0) Table

This table lists the operations that are accessible in lock level 0 (LL0) while the pump is stopped and running. LL0 permits complete access to all programming and operating functions.

 | Stopped | Running
Pump Operations and Programming | LL0 | Any Lock Level
Stop/Start the pump | Yes | Yes
Reset reservoir volume | Yes | No
Prime | Yes | No
Change the lock level | Yes, w/code | No
Change morning dose | No | Yes
Start an extra dose | No | Yes
Start a morning dose | No | Yes
Change continuous rate | Yes | No
Change extra dose | Yes | No
Clear given amount | Yes | No
Biomed Functions
Access to functions | Yes, w/code | No
Extra dose lockout | Yes, w/code | No
Morning dose lockout | Yes, w/code | No
Upstream occlusion Sensor On/Off | Yes, w/code | No

Lock Levels 1 and 2 (LL1, LL2) Table

This table lists the operations that are accessible in lock level 1 (LL1) and lock level 2 (LL2) while the pump is stopped and running. LL1 permits limited control of pump programming and operations. LL2 permits only minimal control of pump operations.

Pump Operations and Programming | Stopped |  | Running
 | LL1 | LL2 | Any Lock Level
Stop/Start the pump | Yes | Yes | Yes
Reset reservoir volume | Yes | Yes | No
Prime | Yes | No | No
Change the lock level | Yes, w/code | Yes, w/code | No
Change morning dose | No | No | Yes*
Start an extra dose | No | No | Yes
Start a morning dose | No | No | Yes
Change continuous rate | Yes* | No | No
Change extra dose | Yes* | No | No
Clear given amount | Yes | No | No

*When in LL1, you can program up to the LL0 value. No programming is allowed in LL2.

2.0 Pump Setup and Programming

Installing or Replacing the Batteries

Use new, AA alkaline batteries such as DURACELL® or EVEREADY® ENERGIZER® batteries to power the pump. The pump retains all programmed values while the batteries are removed.

Dispose of used batteries in an environmentally safe manner, and according to any regulations which may apply.

WARNING:

- Always have new batteries available for replacement. If power is lost, non-delivery of medication will occur, which could compromise patient treatment.

- If the pump is dropped or hit, the battery door or tabs may break. Do not use the pump if the battery door or tabs are damaged because the batteries will not be properly secured; this may result in loss of power and non-delivery of medication, which could compromise patient treatment.

CAUTION: Do not use rechargeable NiCd or nickel metal hydride (NiMH) batteries. Do not use carbon zinc (“heavy duty”) batteries. They do not provide sufficient power for the pump to operate properly.

In order to install or replace the batteries, be sure the pump is Stopped. Then, follow these steps:

1. Push down and hold the arrow button while sliding the door off.

2. Remove the used batteries. Pulling on the end of the battery strap will make battery removal easier.

3. Install the new batteries in the compartment, making sure the battery strap is positioned correctly under the batteries.

NOTE:

- Be sure to match the polarity markings of the new batteries (+ and –) with those labeled in the battery compartment. If you put the batteries in backwards, the display will remain blank, and you will not hear a beep.
- Use two new, AA alkaline batteries to power the pump. You may use any alkaline batteries, including DURACELL® Alkaline and EVEREADY® ENERGIZER® Alkaline, for example.

4. Place the battery door over the battery compartment and slide the door closed.

5. Ensure that the door is latched by trying to remove the door without pressing the arrow button.

NOTE: The power-up sequence will start, the pump will go through an electronic self-test, and the pump will beep 6 times at the end of the power-up sequence. All of the display indicators, the software revision, and each parameter will appear briefly.

WARNING: If a gap is present anywhere between the battery door and the pump housing, the door is not properly latched. If the battery door becomes detached or loose, the batteries will not be properly secured; this could result in loss of power and non-delivery of medication, which could compromise patient treatment.

6. Resume operation of the current program by pressing and holding

to start the pump or proceed to program the pump.

NOTE:

- The life of the batteries is dependent on the amount of medication delivered, delivery rate, battery age, and the temperature.
- At the rate of 100 ml per day, alkaline batteries will usually last about 7 days.
- The power of the batteries will be quickly depleted at temperatures below 10°C (50°F).

CAUTION: Do not store the pump for prolonged periods of time with the batteries installed. Battery leakage could damage the pump.

Watching Power Up

When you install the batteries, the pump will start its power up sequence during which it performs self-tests and displays programmed values. Watch for the following:

- Pump model number and last error code (“LEC”) if any, will appear. (If an error code appears, the pump should be removed from use and returned for service.)
- The software revision will appear.
- The display will turn on, showing a series of blocks. Look for any blank areas, which would indicate a faulty display.
- The display will turn off briefly.
- The pump’s program screens will appear, followed by the current lock level setting. The pump will beep after each screen. If messages appear, see Messages and Alarms Table, Section 5 for further explanation and instruction.
- When power up is complete, 6 beeps will sound, and the pump will be stopped on the main screen.

NOTE: To move quickly through the power-up screens, press

repeatedly. To skip the automatic review entirely, press

If you attempt to skip screens before the pump is powered up, it will not respond.

Changing to Lock Level 0 (LL0)

Before programming the pump, make sure the pump is set to LL0. LL0 allows the clinician to access all programming and operating functions.

1. Make sure the pump is stopped. Press

The current lock level will appear. (If the lock level is already LL0, press

to exit.)

**Text Omitted**

WARNING: Do not disclose to the patient the pump’s security codes or any other information that would allow the patient complete access to all programming and operating functions. Improper programming could compromise patient treatment.

Programming the Pump: General Instructions

WARNING: System delivery inaccuracies beyond the stated accuracy may occur as a result of back pressure or fluid resistance, which depends upon temperature, medication viscosity, catheter size, extension set tubing, and orientation of the pump system.

The procedure for changing a programmed setting is similar for most programming screens.

- Make sure the pump is stopped and in lock level 0.
- To begin programming, start at the main screen and press

- To change a setting, press

or

until the desired setting appears. (Press and hold these keys to change values with increasing speed.)

- Press

within 25 seconds to confirm a change or the screen will revert to the previous setting.

- If any key other than

is pressed, Value not saved will appear. Press

to return to the screen being programmed, scroll to the desired value, and press

- Press

to advance to the next screen.

- To leave a setting unchanged, press

to go to the next screen.

Delivery Methods

WARNING: Programming the pump at a delivery rate other than what is prescribed will cause over- or under-delivery of medication, which could compromise patient treatment. Please refer to the prescribing information for DUOPA for dosage and administration information.

The CADD-Legacy® 1400 pump offers 3 methods of delivery:

- Continuous rate
- Extra dose
- Morning dose

The following graph illustrates the combined delivery methods. The continuous rate, extra dose, and morning dose are programmed as described in this section. Ranges and programming increments are listed in the Specifications in Section 5.

Programming Screens

These are the programming screens for the CADD-Legacy® 1400 pump. Descriptions of the screens follow.

Reservoir Volume (ml)

Continuous Rate (ml/hr)

Extra Dose (ml)

Given (ml)

Reservoir Volume

NOTE: The default setting for Reservoir Volume is Not in Use. Programming a reservoir volume value is not required for general use, but is available at provider discretion.

If you wish to use the reservoir volume feature, enter the volume of medication contained in the filled medication cassette reservoir. The reservoir volume value decreases as the pump delivers medication or as you prime the tubing. When you change the medication cassette reservoir, reset the reservoir volume value on this screen. If you do not wish to use the reservoir volume feature, scroll down to Not In Use (located before 1 and after 9999 in the range of values).

The reservoir volume value could be set higher than the capacity of the medication cassette reservoir. Be sure to program the reservoir volume to reflect the actual volume in the reservoir.

Continuous Rate

Enter the continuous rate of medication delivery in ml/hr. The maximum rate is 20 ml/hr. If the prescription does not call for a continuous rate, enter zero.

NOTE: If you intend to run the pump in lock level 1 so the continuous rate can be varied, you should enter the maximum allowable rate while programming in lock level 0. After programming, you may then change to lock level 1 and decrease the rate to its starting value. See Programming with Upper Limits, Adjusting Doses in LL1 at the end of Section 2.

Extra Dose

Enter the amount of medication to be delivered when the patient presses

If the prescription does not call for an extra dose, enter zero.

NOTE: If you intend to run the pump in lock level 1 so the extra dose can be varied, you should enter the maximum allowable dose while programming in lock level 0. After programming, you may then change to lock level 1 and decrease the dose to its starting value. See Programming with Upper Limits, Adjusting Doses in LL1 at the end of Section 2.

Given

This screen shows the total amount of medication delivered since the last time this value was cleared. The amount shown is rounded to the nearest 0.05 ml. If this value reaches 99999.95, it automatically returns to 0 and continues counting. When using the pump’s

key, the amount of medication used is not included in the Given amount.

Other Programming Information

The morning dose should be programmed separately following programming of the above. Information on programming the morning dose can be found later in this section.

Programming Delivery

WARNING: Programming the pump at a delivery rate other than what is prescribed will cause over- or under-delivery of medication, which could compromise patient treatment. Please refer to the prescribing information for DUOPA for dosage and administration information.

To program the pump, enter the prescribed values.

1. Begin at the main screen.

- Make sure the pump is in LL0.
- Make sure STOPPED appears on the main screen.
- Press

to begin.

2. Enter the reservoir volume (optional – not required for general use).

NOTE: The default setting for Reservoir Volume is Not in Use. Programming a reservoir volume value is not required for general use, but is available at provider discretion.

- Press

or

to select the volume in the filled medication cassette reservoir. (If you do not wish to use the reservoir volume feature, scroll down to Not In Use located before 1 or after 9999.)

- Press

- Press

3. Enter the continuous rate.

- Press

or

to select the desired continuous rate.

- Press

- Press

4. Enter the extra dose amount.

- Press

or

to select the desired extra dose amount.

- Press

- Press

NOTE: If required, program the extra dose lockout time, as instructed in Section 4, Biomed Functions.

5. Clear the amount given.

- Press

if you wish to clear the amount given.

- Press

6. Review the program.

Press

repeatedly to review the programming screens. If you need to reprogram a setting, press

until the appropriate screen appears and change the setting as described in this section.

Programming a Morning Dose

To program a morning dose the pump must be running and a medication cassette reservoir must be attached.

To program a morning dose

1. Make sure the pump is running and in LL0 or LL1. Start the pump, if necessary.
NOTE: In LL0, programming in the full range is possible. In LL1, you can program up to the LL0 value.

2. Press

The current morning dose value will appear.

3. Press

or

to select the desired morning dose value.

4. Press

to enter the value into the pump’s memory. (If desired, press

again to begin delivering the morning dose.)

Once entered, the morning dose amount is retained in the pump’s memory. The patient can then press

twice to display and deliver the morning dose.

NOTE: If required, program the morning dose lockout time, as instructed in Section 4, Biomed Functions.

Removing a Medication Cassette Reservoir

WARNING: Clamp the fluid path tubing and/or disconnect the tubing from the enteral access device before removing the medication cassette reservoir from the pump to prevent uncontrolled delivery of medication, which could compromise patient treatment.

To remove the medication cassette reservoir from the pump

1. Stop the pump.

2. Close the tubing clamp. If necessary, disconnect the tubing from the enteral access device.

3. Insert a coin into the slot in the cassette latch and turn it clockwise. The latch will pop out when you unlatch the cassette (the part of the medication cassette reservoir that attaches to the bottom of the pump).

4. A continuous alarm will sound and the pump will display No Disposable, Clamp Tubing (the pump is not sensing proper cassette attachment). The alarm may be silenced by pressing

or

5. Remove the cassette hooks from the pump hinge pins.

Attaching a Medication Cassette Reservoir

Obtain a new, filled medication cassette reservoir.

WARNING:

- Use only approved DUOPA medication cassette reservoirs to maintain pump accuracy and assure proper pump operations.
- Use only extension sets approved for use with DUOPA, paying particular attention to all warnings and cautions associated with their use.

After attaching the medication cassette reservoir, proceed to the reservoir volume screen to reset the value for the volume, and then prime the tubing.

To attach the medication cassette reservoir to the pump

1. Clamp the tubing.
2. Insert the cassette hooks into the hinge pins on the pump.
3. Place the pump upright on a firm, flat surface. Press down so the cassette fits tightly against the pump.

4. Insert a coin into the slot in the cassette latch, push in, and turn counterclockwise until the line on the latch lines up with the arrow on the side of the pump and you feel the latch click into place.

WARNING: Attach the cassette properly. The cassette is the part of the medication cassette reservoir that attaches to the pump. A detached or improperly attached cassette could result in unintended delivery of medication, which could compromise patient treatment.

5. Gently twist, push, and pull on the medication cassette reservoir to make sure it is firmly attached. If the cassette is not secure, repeat the procedure from step 1.

Priming the Tubing and Connecting to the Patient

WARNING: Do not prime the fluid path with the tubing connected to a patient as this could result in over-delivery of medication, which could compromise patient treatment.

The pump must be stopped and in LL0 or LL1 in order to prime the fluid path. If the pump is in LL2, you cannot prime the fluid path.

NOTE: If you are not changing the medication cassette reservoir but wish to prime the fluid path, you may follow the same procedure.

1. Make sure the tubing is disconnected from the patient and the tubing clamp is open.

2. Press and hold

You will hear a single beep, and the word Prime and 3 sets of dashes, each accompanied by a beep, will appear on the display.

3. After Prime and 3 sets of dashes appear, release

4. Press and hold

again to fill the fluid path. The screen displays Priming . . . and you will hear a short beep each time the pump goes through a delivery cycle.

NOTE: Medication delivered during priming is subtracted from the reservoir volume, but is not added to the given screen since this amount is not delivered to the patient.

5. If the tubing is not yet fully primed, press and hold

again. If the tubing is primed, press

to return to the main screen.

NOTE: Each time you press and hold

you pump a maximum of 1 ml of medication into the tubing. The pumping action will stop automatically when 1 ml has been delivered. Release

if you finish priming the fluid path sooner. If the fluid path is not fully primed, repeat the above priming procedure.

6. Connect the tubing to the patient’s enteral access device.

7. Set the lock level for the patient (see Setting the Lock Level for the Patient in this section).

Setting the Lock Level for the Patient

The lock level must be changed to LL1 or LL2 to prevent the patient from having complete access to all programming and operating functions.

NOTE: You may change the lock level at any time by stopping the pump and following the procedure below.

To change the lock level

**Text Omitted**

WARNING: Do not disclose to the patient the pump’s security codes or any other information that would allow the patient complete access to all programming and operating functions. Improper programming could compromise patient treatment.

Programming with Upper Limits, Adjusting Doses in Lock Level 1

If a prescription allows for the continuous rate, extra dose, or morning dose to be adjusted during the course of therapy, you may wish to operate the pump in LL1. Then, when necessary, you can adjust values up to the maximum value that was programmed in LL0.

Programming the pump to use this feature

1. During initial programming in LL0, enter the upper limit values for the continuous rate, extra dose and/or morning dose. (These will be the maximum values when the pump is in LL1.)
2. After you are finished programming, change the lock level to LL1.
3. Decrease the continuous rate, extra dose and/or morning dose to its starting value, then press

Adjusting the rate or dose while the pump is in use

- If it becomes necessary to increase or decrease the continuous rate, and/or extra dose during the course of therapy, stop the pump but remain in LL1.
- To increase or decrease the morning dose, the pump must be in LL1, but it must remain running.

1. To change the continuous rate or extra dose, press

until the continuous rate or extra dose screen appears.

To change the morning dose, press

2. Press

or

to select the desired value, then press

NOTE: You will not be able to adjust the continuous rate, extra dose, or morning dose beyond the value originally programmed in LL0.

3. Restart the pump if appropriate.

3.0 Operating the Pump

Starting the Pump

When you start the pump, programmed values will be automatically reviewed. Then medication delivery will begin as programmed, and RUN will appear on the main screen. If the pump will not start, a message will appear on the display. Refer to the Messages and Alarms Table in Section 5.

CAUTION: Prior to starting medication delivery, inspect the fluid path for kinks, a closed clamp, or other obstruction. An undetected occlusion may result in under- or non-delivery and/or nuisance alarms.

To start the pump

1. Press and hold

Starting and 3 sets of dashes appear on the display; then the dashes disappear one-by-one, each accompanied by a single beep.

2. Release

after the last set of dashes disappears, and the pump beeps. All of the programming screens appear for your review one after the other.

Stopping the Pump

Stopping the pump stops delivery. When the pump is stopped, STOPPED will appear on the main screen, and you will hear 3 beeps every 5 minutes.

To stop the pump

1. Press and hold

Stopping and 3 sets of dashes appear one-by-one on the pump’s display, each accompanied by a single beep.

2. Release

after the third set of dashes appears and the pump beeps.

Turning the Pump On/Off

When the pump is stopped, you may put the pump into a low power state by turning it off. The pump may be turned off when it is disconnected from the patient and it is going to be stored for short periods of time.

CAUTION: Do not store the pump for prolonged periods of time with the batteries installed. Battery leakage could damage the pump.

To turn the pump off

1. Press and hold

Turning off and 3 sets of dots will appear one-by-one on the pump’s display, each accompanied by a single beep.

2. Release

The display turns off.

To turn the pump on

1. Press and hold

until the display turns on.

2. Release

The pump will power up and automatically review all screens.

Starting a Morning Dose

A morning dose may be delivered in any lock level while the pump is running. It allows you to deliver a specified amount of medication, as a loading dose for example.

If the patient attempts to deliver a morning dose during the lockout time, the pump will not deliver the dose. The lockout time is determined by the value entered in Morning Dose Lockout, in biomed functions. The extra dose lockout setting has no effect on morning dose frequency. A morning dose may be stopped in progress.

NOTE: A morning dose cannot be started while an extra dose or another morning dose is in progress.

To start a morning dose

To program a morning dose, the pump must be running and a medication cassette reservoir must be attached.

NOTE: The

key must be pressed twice for morning dose delivery to start.

1. Make sure the pump is running (in any lock level). Start the pump if necessary.
2. Press

The current morning dose value (or the default value of 0 ml) will appear UNLESS the morning dose is currently locked out (in which case the screen will not appear). If the desired morning dose amount appears in the display, press

again to begin delivery.

NOTE: If the desired morning dose amount does not appear in the display, program the desired morning dose amount as instructed in Section 2, Pump Setup and Programming.

The screen will show the value decreasing as the morning dose is delivered.

Starting an Extra Dose

If an extra dose has been programmed, the patient may start an extra dose while the pump is running. The amount delivered is added to the amount provided by the continuous rate.

If the patient attempts to deliver an extra dose during the lockout time, the pump will not deliver the dose. The lockout time is determined by the value entered in Extra Dose Lockout, in biomed functions.

NOTE: An extra dose cannot be started while another extra dose or a morning dose is in progress.

To start an extra dose

1. Make sure the pump is running (in any lock level). Start the pump if necessary.
2. Press

Two beeps will sound and the pump will begin delivering the extra dose.
As the extra dose is delivered, the main screen will show DOSE in place of RUN.

Stopping an Extra Dose or Morning Dose

An extra dose or morning dose can be stopped in progress. The pump may be in any lock level.

To stop an extra dose or morning dose in progress

- Press and hold

to stop the pump. All delivery is stopped, including the continuous rate.

Resetting the Reservoir Volume

NOTE: The default setting for Reservoir Volume is Not in Use. Programming a reservoir volume value is not required for general use, but is available at provider discretion.

To reset the reservoir volume to the value programmed in LL0, the pump may be in any lock level.

1. Stop the pump.

2. Press

to display the reservoir volume screen.

3. Press

to reset the volume to the programmed value.

4.0 Biomed Functions

Overview: Accessing the Biomed Functions and Programming the Lockouts

The biomed functions are pump configurations that are less frequently changed. The biomed functions are accessible only when the pump is stopped and in lock level 0 (LL0).

To access the Biomed Functions

**Text Omitted**

WARNING: Do not disclose to the patient the pump’s security codes or any other information that would allow the patient complete access to all programming and operating functions. Improper programming could compromise patient treatment.

4. Press

to select the setting you wish to view or change, then follow the instructions in this section for the appropriate screen.

NOTE: To leave a biomed function setting unchanged, press

5. To exit the biomed functions, press

until you get to the screen that reads, NEXT for Biomed, ENTER for Main.

6. Press

to return to the main screen.

Extra Dose Lockout

The extra dose lockout time determines how often a patient can receive an extra dose of medication. The lockout time is the minimum amount of time which must elapse between the start of one dose and the start of the next.

To program an extra dose lockout time

1. With the pump stopped and in LL0, access biomed functions. (Refer to the beginning of the Biomed Functions section for instructions on how to access biomed functions.)

2. Press
until Extra Dose appears.
3. Press
or
to scroll to the desired lockout time. The default lockout time is 1 hour.
4. Press
to enter the value.

CAUTION: When you enter a new value, any lockout time already in effect will be cleared. An extra dose could be requested and delivered immediately upon starting the pump, which may result in over-delivery of medication.

Morning Dose Lockout

The morning dose lockout time determines how often a patient can receive a morning dose. The lockout time is the minimum amount of time which must elapse between the start of one dose and the start of the next.

To program a morning dose lockout time

1. With the pump stopped and in LL0, access biomed functions. (Refer to the beginning of the Biomed Functions section for instructions on how to access biomed functions.)

2. Press
until Morning Dose appears.
3. Press
or
to scroll to the desired lockout time.
4. Press
to enter the value.

CAUTION: When you enter a new value, any lockout time already in effect will be cleared. A morning dose could be requested and delivered immediately upon starting the pump, which may result in over-delivery of medication.

Upstream Occlusion Sensor On/Off

The upstream occlusion sensor can be set to On or Off. If this screen is set to On, and an occlusion in the medication cassette reservoir is detected, an alarm will sound, delivery will stop, and the display will show Upstream Occlusion.

CAUTION: When the upstream occlusion sensor is turned off, the pump will not detect occlusions in the medication cassette reservoir. Periodically inspect the medication cassette reservoir for decreasing volume. Undetected occlusions could result in under- or non-delivery of medication.

1. With the pump stopped and in LL0, access biomed functions. (Refer to the beginning of the Biomed Functions section for instructions on how to access biomed functions.)

2. Press
until Upstream Sensor appears.
3. Press
or
to select Off or On.
4. Press
to enter the change.

5.0 Reference

Messages and Alarms, Alphabetical List

Messages and Alarms | Description / Corrective Action
[No message] Two-tone alarm | With no AC adapter attached, the batteries have been removed while the pump is running. The pump is now stopped and unpowered. Install batteries to silence the alarm. OR Batteries were removed within approximately 15 seconds after stopping the pump. Install new batteries to silence the alarm, if desired. Otherwise, the alarm will stop within a short period of time.
[Screen displays current pump status] Two-beeps (long-short) | The medication cassette reservoir is not aligned with the pump or medication is not flowing from the medication bag inside the reservoir to the pumping mechanism. Press or to silence the alarm. The pump continues to run. Make sure the medication cassette reservoir is properly aligned with the pump and medication is flowing from the medication bag to the pumping mechanism. Very cold or extremely thick medication may cause this alarm as well. Allow the medication cassette reservoir to thaw to room temperature before attaching to the pump.
Battery Depleted Two-tone alarm | The battery power is too low to operate the pump. The pump is now stopped.; - Change the batteries immediately. - Press and hold; to restart the pump.
Battery Removed Pump won’t run Two-tone alarm | With the AC adapter attached, the AA batteries have been removed while the pump is running, or you have tried to start the pump with depleted batteries. The pump is now stopped. Press or to silence the alarm. Reinstall batteries or install new batteries. Press and hold to restart the pump.
Error Two-tone alarm | An error has occurred. Remove the pump from service and contact Smiths Medical to return the pump for service.
High Pressure Two-tone alarm | The pump has detected high pressure, which may be resulting from a downstream blockage, kink in the fluid path, or a closed clamp. Remove the occlusion to resume operation. Or, press or to stop the pump and silence the alarm for 2 minutes, then remove the occlusion and restart the pump.
Key pressed, Please release Two-tone alarm | If a key is being pressed, stop pressing it. If the alarm persists, close the tubing clamp and remove the pump from use. Contact Smiths Medical to return the pump for service.
LowBat Three two-tone beeps every 5 minutes | The batteries are low, but the pump is still operable.; - Change the batteries soon.
Motor Locked, remove all power Two-tone alarm | Batteries are depleted and the pump was powered up with the AC adapter. Install new AA batteries, reconnect the AC adapter, and restart the pump.
No Disposable, Clamp Tubing Two-tone alarm | The disposable (medication cassette reservoir) was removed. The pump is not sensing proper cassette attachment. Clamp the tubing and disconnect from the enteral access device. A medication cassette reservoir must be properly attached in order for the pump to run. Press or to silence the alarm.
No Disposable, Pump won’t run Two-tone alarm | You have tried to start the pump without a disposable (medication cassette reservoir) attached. A medication cassette reservoir must be properly attached in order for the pump to run. Press or to silence the alarm.
Power lost while pump was on Two-tone alarm | The pump was running when power was removed. Stop the pump before changing the batteries or removing the power source. Press or to silence the alarm.
Programming Incomplete Two-tone alarm when starting the pump | A rate or dose must be programmed to start the pump. Press or to silence the alarm.
Reservoir Volume Empty Two-tone alarm | The reservoir volume has reached 0.0 ml. Press or to silence the alarm. Then install a new medication cassette reservoir if appropriate and reset the reservoir volume.
RUN ResVol Low Three single beeps | The reservoir volume is low. Change the medication cassette reservoir soon. See Reservoir Volume Alarm in Section 1 for further details.
Service Due Two-tone alarm | The pump is functional, but is due for service based on clock battery age or total motor revolutions. This screen appears in LL0 for 60 days and then in all lock levels until returned for service.
Upstream Occlusion Two-tone alarm | If the upstream occlusion sensor is set to On and an occlusion in the medication cassette reservoir is detected, the upstream occlusion alarm will sound. Press or to stop the pump and silence the alarm for 2 minutes, then remove the occlusion and restart the pump. You may have to detach the cassette from the pump, then reattach it.
Value not saved | A value was not saved by pressing Press to resume programming. Verify all programming screens before moving to the next screen or starting the pump.

What if the pump is dropped or hit?

Immediately do the following:

- Check the cassette latch on the side of the pump and make sure the line on the latch lines up with the arrow on the side of the pump.

- Gently twist, push, and pull on the medication cassette reservoir to make sure it is still firmly attached.

- Check the battery door to make sure it is still firmly attached.

If the medication cassette reservoir or the battery door is loose or damaged, do not use the pump. Immediately stop the pump, close the tubing clamp, and contact Smiths Medical.

WARNING: If the pump is dropped or hit, inspect the pump for damage. Do not use a pump that is damaged or is not functioning properly, as this could compromise patient treatment.

- If the pump is accidentally dropped in water, retrieve it quickly, dry it off with a towel, and contact Smiths Medical.

Cleaning the Pump and Accessories

CAUTION:

- Do not immerse the pump in cleaning fluid or water. Do not allow solution to soak into the pump, accumulate on the keypad, or enter the battery compartment. Moisture buildup inside the pump may damage the pump.
- Do not clean the pump with acetone, other plastic solvents, or abrasive cleaners, as damage to the pump may occur.

NOTE: Refer to the Instructions for Use for each accessory before proceeding with cleaning.

The following solutions may be used to clean the pump and accessories, unless otherwise specified:

- Soap solution
- Benzalkonium chloride concentrate (0.13%)
- Glutaral concentrate, USP (2%)
- 10% solution of household bleach (one part household bleach to 9 parts water)
- Alcohol, USP (93%)
- Isopropyl Alcohol, USP (99%)
- Chlorhexidine gluconate (4%)
- PDI Super Sani-Cloth®
- MadaCide, Mada Medical

1. Dampen a soft, lint-free cloth with cleaning solution. Apply the solution to the exterior surface of the pump (per manufacturer’s instructions). Do not allow the solution to soak into the pump or accessory.
2. Wipe the entire surface dry with another soft, lint-free cloth. Allow the pump to dry completely before use.

Cleaning the Battery Contacts

Routinely clean the battery contacts, possibly as part of the preventative maintenance cycle, to remove buildup of foreign material on the contacts.

Use the following to clean the battery contacts:

- Cotton swab wetted with Isopropyl Alcohol (70% minimum)
  NOTE: Do not use an alcohol formulation that contains components other than alcohol and water.
  OR

- Pre-moistened alcohol swab

1. Using a swab wetted with alcohol, rub the entire battery contact for a minimum of 10 back and forth cycles (20 total wipes over the contact).
2. Using a clean surface of the swab, repeat process for second battery contact.
3. Using a clean swab wetted with alcohol, rub each battery contact again, a minimum of 4 back and forth cycles (8 total wipes over the contact).
4. Allow the contacts to dry completely before use.

Exposure to Radiation, Ultrasound, Magnetic Resonance Imaging (MRI), or Use near ECG Equipment

CAUTION:

- Do not expose the pump to therapeutic levels of ionizing radiation as permanent damage to the pump’s electronic circuitry may occur. The best procedure to follow is to remove the pump from the patient during therapeutic radiation sessions. If the pump must remain in the vicinity during a therapy session, it should be shielded, and its ability to function properly should be confirmed following treatment.
- Do not expose the pump directly to ultrasound, as permanent damage to the electronic circuitry may occur.
- Do not use the pump in the vicinity of magnetic resonance imaging (MRI) equipment as magnetic fields may adversely affect the operation of the pump. Remove the pump from the patient during MRI procedures and keep it at a safe distance from magnetic energy.
- This pump may interfere with ECG equipment. Monitor ECG equipment carefully when using this pump.

Continuous Rate Scroll Ranges

Starting Value | Increment | Maximum
0.0 ml/hr | 0.1 ml/hr | 20.0 ml/hr

Extra Dose, Morning Dose Scroll Ranges

Extra Dose
increment | max.
0.1 ml | 9.9 ml
Morning Dose
increment | max.
0.1 ml | 20 ml

Technical Description

Standards used in Development of the Pump

The following standards were used in whole or part in the development of the pump:

IEC 60601-1 (1988), (2nd Edition, 1988) Medical Electrical Equipment, Part 1: General Requirements for Safety. Amendment 1 (1991), Amendment 2 (1995).

EN 60601-1 (1990), Medical Electrical Equipment, Part 1: General Requirements for Safety. Amendment A1 (1993), Amendment A13 (1996), Amendment A2 (1995).

IEC 60601-1-2 (2007), Medical Electrical Equipment, Part 1-2: General Requirements for Safety – Collateral Standard: Electromagnetic Compatibility – Requirements and Tests.

EN 60601-1-2 (2007), Medical Electrical Equipment, Part 1-2: General Requirements for Safety – Collateral Standard: Electromagnetic Compatibility – Requirements and Tests.

The following are reference test methods applied to IEC/EN 60601-1-2:

IEC/EN 61000-4-2, Electromagnetic Compatibility (EMC), Part 4: Testing and measurement techniques. Section 2: Electrostatic Discharge immunity test. Basic EMC Publication.

IEC/EN 61000-4-3, Electromagnetic Compatibility (EMC), Part 4: Testing and measurement techniques. Section 3: Radiated, radio frequency, electromagnetic fields immunity test. Basic EMC Publication.

IEC/EN 61000-4-4, Electromagnetic Compatibility (EMC), Part 4: Testing and measurement techniques. Section 4: Electrical fast transients/bursts immunity test. Basic EMC Publication.

IEC/EN 61000-4-5, Electromagnetic Compatibility (EMC), Part 4: Testing and measurement techniques. Section 5: Surge immunity test. Basic EMC Publication.

IEC/EN 61000-4-8, Electromagnetic Compatibility (EMC), Part 4: Testing and measurement techniques. Section 8: Power frequency magnetic field immunity test.

IEC/EN 61000-4-11, Electromagnetic compatibility (EMC) - Part 4: Testing and measuring techniques - Section 11: Voltage dips, short interruptions and voltage variations immunity tests.

IEC 60601-2-24 (1998), Medical Electrical Equipment, Part 2-24: Particular Requirements for Safety of Infusion Pumps and Controllers.

EN 60601-2-24 (1998), Medical Electrical Equipment, Part 2-24: Particular Requirements for Safety of Infusion Pumps and Controllers.

IEC 60601-1-4 (2000), Medical Electrical Equipment, Part 1: General Requirements for Safety – Collateral Standard: Programmable electrical medical systems.

EN 60601-1-4 (1996), Medical Electrical Equipment, Part 1-4: General Requirements for Safety – Collateral Standard: Programmable electrical medical systems. Amendment A1: 1999.

EN 980 (2008), Graphical symbols for use in the labeling of medical devices.

FCC Part 15 Subpart B, Radiofrequency Devices, Unintentional Radiators.

RTCA/DO -160C, Radiated Emissions Only, Category A & Z Limit.

EN 55011 (2007), Limits and Methods of Measurement of Radio Interference Characteristics of Industrial, Scientific and Medical (ISM) Equipment. Amendment A2: 2007. (Equivalent to CISPR 11: 2003 + Amendment A2: 2006).

CISPR11 (2009), Limits and methods of measurement of electromagnetic disturbance characteristics of industrial, scientific and medical (ISM) radio frequency equipment. Amendment 1 (1996) Amendment 2 (1996).

For CISPR11 tests, the pump was fitted with an administration set with its inlet connected to a 250 ml bag and its outlet routed back to the bag forming a closed loop system. A total of 6 feet of tubing was used to form the closed loop.

Specifications (Nominal)

General Pump Specifications
Resolution | medication cassette reservoir: 0.05 ml per pump activation nominal
Size | 4.1 cm × 9.5 cm × 11.2 cm [1.6 in. × 3.8 in. × 4.4 in.] excluding medication cassette reservoir
Weight | 392 g [13.8 oz.] including 2 AA batteries, empty 100 ml medication cassette reservoir, excluding other accessories
Classification (IEC 60601-1) | CF Class II
Moisture protection | Splashproof (IPX4)
Pump alarms | Low battery power; depleted battery power; battery dislodged; pump stopped; pump fault; low reservoir volume; high pressure; disposable not attached when run attempted; motor locked; upstream occlusion; reservoir volume empty; program incomplete; remote dose cord removed; key stuck; disposable detached.
Maximum infusion pressure | 40 psi [2.76 bar]
Maximum time to occlusion alarm (actual test data) | DUOPA (carbidopa and levodopa) enteral suspension: 10 hours 30 minutes
Bolus volume at occlusion alarm pressure | 0.05 ml resolution medication cassette reservoir: <1.1 ml
Power sources | AC adapter; Two AA alkaline batteries
Battery life | The expected life of 2 AA batteries is 100 hours at 100 ml/16 hours, or approximately 14 days at 10 ml/day (nominal). This estimate is based on laboratory tests conducted at room temperature using two new batteries. Actual battery life will vary depending on the brand of battery, battery shelf life, temperature conditions, and delivery rate. It is recommended that two new AA batteries be kept available for replacement if necessary. An internal battery powers the clock. When it is depleted, it cannot reliably maintain the clock time. This battery must be replaced by the manufacturer. The internal battery has an expected life of 5 years.
System operating temperature | 2°C to 40°C (36°F to 104°F)
System storage and transportation temperature | -20°C to 60°C (-4°F to 140°F)
When shipping, use pump case.
System delivery accuracy (DUOPA [carbidopa and levodopa] enteral suspension):
Therapy^1 | ±10%
Continuous rate^2 | ±10% @ flow rates 0.4 ml/hr to 20 ml/hr
Extra dose^2 | ±10%
Morning dose^2,3 | ±10%
Accessories: 100 ml medication cassette reservoir with 36” 0.10” I.D. tube
^1Therapy delivery accuracy: program to deliver a 10 ml morning dose with a 5 ml/hr continuous rate and three 3 ml extra doses, with a total of 100 ml of medication delivered. Pumps were evaluated in latch down, upside down, and horizontal position. The medication cassette with DUOPA (carbidopa and levodopa) enteral suspension is initially cold (approx. 2°C). Remove cassette from refrigerator, wait 20 minutes, then conduct the test at nominal temperature.^2
^2At nominal temperature (23°C ± 5°C)
^3An additional -4% change may be seen when cassette starting temperature is 2°C and placed at room temperature (23°C ± 5°C) for 20 minutes prior to use.

WARNING: System delivery inaccuracies beyond the stated accuracy may occur as a result of back pressure or fluid resistance, which depends upon temperature, medication viscosity, catheter size, extension set tubing, flow rate, and orientation of the pump system.

System definition | System is defined as a CADD-Legacy® 1400 pump with attached medication cassette reservoir supplied by AbbVie
High pressure alarm | 26 ± 14 psi [1.79 ± 0.97 bar]
Maximum volume infused under single fault condition | medication cassette reservoir: 0.2 ml.
Delivery rate during priming | Approx. 125 ml/hr

Delivery Specifications
Reservoir volume | 1 to 9999 or Not In Use; programmable in 1 ml increments, displayed in 0.1 ml increments Default: Not In Use
Continuous rate | 0 to 20 ml/hr in 0.1 ml/hr increments Default: 0.1 ml/hr
Extra dose | 0 to 9.9 ml in 0.1 ml increments Delivery rate (continuous rate + extra dose): 40 ml/hr Default: 0 ml
Given | 0 to 99999.95 in 0.05 unit increments
Morning dose | 0 to 20.00 ml in 0.1 ml increments Delivery rate (continuous rate + morning dose): 40 ml/hr Default: 0 ml

Biomed Functions
Extra dose lockout | 15 minutes to 24 hours in 15 minute increments Default: 1 hour
Morning dose lockout | 1 to 24 hours in 1 hour increments Default: 20 hours
Upstream sensor | Off On Default: Off

Accuracy Test Results

The following graphs are designed to show flow accuracy of the infusion system plotted against given time periods. The medication cassette reservoir used for flow accuracy tests was supplied by AbbVie.

Flow rate immediately following startup
Time Interval: | 0.5 min
Total Time: | 120 min
Programmed Rate: | 5 ml/hr
Reservoir Used: | 100 ml medication cassette reservoir

Short term flow rate error
Programmed Rate: | 5 ml/hr
Average Flow Rate: | 4.76 ml/hr
Mean Flow Error: | –4.65%
Reservoir Used: | 100 ml medication cassette reservoir

Electromagnetic Emissions and Immunity Declarations

Electromagnetic emissions declaration
The Pump is intended for use in the electromagnetic environment specified below. The customer or the user of the Pump should assure that it is used in such an environment.
Emissions test | Compliance | Electromagnetic environment – guidance
RF emissions, CISPR 11 | Group 1 | The Pump uses RF energy only for its internal function. Therefore, its RF emissions are very low and are not likely to cause any interference in nearby electronic equipment.
RF emissions, CISPR 11 | Class B | The Pump is suitable for use in all establishments, including domestic establishments and those directly connected to the public low-voltage power supply network that supplies buildings used for domestic purposes.
Harmonic emissions IEC 61000-3-2 | Not applicable
Voltage fluctuations/ flicker emissions IEC 61000-3-3 | Not applicable

Compliance using:

1. 115VAC/60HZ to 8VDC Power Adapter (US) with a cord length of 274 ± 10 cm (108 ± 4 in).
2. Remote Dose Cord with a length of 152 ± 5 cm (60 ± 2 in).

WARNING:

- The Pump should not be used adjacent to or stacked with other equipment. If adjacent or stacked use is necessary, the user should verify normal operation of the pump in the configuration in which it is to be used.
- The use of power supplies and a remote dose cord other than those listed in the electromagnetic emissions declaration may result in increased emissions or decreased immunity of the Pump.

Electromagnetic immunity declaration
The Pump is intended for use in the electromagnetic environment specified below. The customer or the user of the Pump should assure that it is used in such an environment.
Immunity test | IEC 60601 test level | Compliance level | Electromagnetic environment – guidance
Electrostatic discharge (ESD) IEC 61000-4-2 | ±8 kV contact ±15 kV air | ±8 kV contact ±15 kV air | Floors should be wood, concrete or ceramic tile. If floors are covered with synthetic material, the relative humidity should be at least 30%.
Electrical fast transient/burst IEC 61000-4-4 | ±2 kV for power supply lines ±1 kV for input/output lines | ±2 kV for power supply lines Not applicable | Mains power quality should be that of a typical commercial or hospital environment.
Surge IEC 61000-4-5 | ±1 kV differential mode ±2 kV common mode | ±1 kV differential mode ±2 kV common mode | Mains power quality should be that of a typical commercial or hospital environment.
Voltage dips, short interruptions and voltage variations on power supply input lines IEC 61000-4-11 | <5 % UT (>95 % dip in UT) for 0,5 cycle 40 % UT (60 % dip in UT) for 5 cycles 70 % UT (30 % dip in UT) for 25 cycles <5 % UT (>95 % dip in UT) for 5 sec | <5 % UT (>95 % dip in UT) for 0,5 cycle 40 % UT (60 % dip in UT) for 5 cycles 70 % UT (30 % dip in UT) for 25 cycles <5 % UT (>95 % dip in UT) for 5 sec | Mains power quality should be that of a typical commercial or hospital environment. If the user of the Pump requires continued operation during power mains interruptions, it is recommended that the Pump be powered from an uninterruptible power supply or a battery.
Power frequency 50/60 Hz) magnetic field IEC 61000-4-8 | 3 A/m | 400 A/m (IEC 60601-2-24) | Power frequency magnetic fields should be at levels characteristic of a typical location in a typical commercial or hospital environment.
NOTE: UT is the a.c. mains voltage prior to application of the test level.

Electromagnetic immunity declaration

The Pump is intended for use in the electromagnetic environment specified below. The customer or the user of the Pump should assure that it is used in such an environment.

Immunity test

IEC 60601
test level

Compliance
level

Electromagnetic environment – guidance

Portable and mobile RF communications equipment should be used no closer to any part of the Pump, including cables, than the recommended separation distance calculated from the equation applicable to the frequency of the transmitter.

Conducted RF
IEC 61000-4-6

3 Vrms
150 kHz to
80 MHz

10 Vrms

Recommended separation distance
d=0.27*P 1/2

Radiated RF
IEC 61000-4-3

3 V/m
80 MHz to
2,5 GHz

10 V/m

d=0.27*P 1/2 80MHz to 800 MHz
d=0.54*P 1/2 800MHz to 2,5 GHz
Where P is the maximum output power rating of the transmitter in watts (W) according to the transmitter manufacturer and d is the recommended separation distance in meters (m).
Field strengths from fixed RF transmitters, as determined by an electromagnetic site survey,a should be less than the compliance level in each frequency range.b
Interference may occur in the vicinity of equipment marked with the following symbol:

NOTE 1: At 80 MHz and 800 MHz, the higher frequency range applies.

NOTE 2: These guidelines may not apply in all situations. Electromagnetic propagation is affected by absorption and reflection from structures, objects and people.

aField strengths from fixed transmitters, such as base stations for radio (cellular/cordless) telephones and land mobile radios, amateur radio, AM and FM radio broadcast and TV broadcast cannot be predicted theoretically with accuracy. To assess the electromagnetic environment due to fixed RF transmitters, an electromagnetic site survey should be considered. If the measured field strength in the location in which the Pump is used exceeds the applicable RF compliance level above, the Pump should be observed to verify normal operation. If abnormal performance is observed, additional measures may be necessary, such as reorienting or relocating the Pump.

bOver the frequency range 150 kHz to 80 MHz, field strengths should be less than 10 V/m.

Recommended separation distances between portable and mobile RF communications equipment and the Pump
The Pump is intended for use in an electromagnetic environment in which radiated RF disturbances are controlled. The customer or the user of the Pump can help prevent electromagnetic interference by maintaining a minimum distance between portable and mobile RF communications equipment (transmitters) and the Pump as recommended below, according to the maximum output power of the communications equipment.
Rated maximum output power of transmitter | Separation distance according to frequency of transmitter m
W | 150 kHz to 80 MHz d=0.27*P1/2 | 80 MHz to 800 MHz d=0.27*P1/2 | 800 MHz to 2,5 GHz d=0.54*P1/2
0.01 | 0.03 | 0.03 | 0.05
0.1 | 0.09 | 0.09 | 0.17
1 | 0.27 | 0.27 | 0.54
10 | 0.85 | 0.85 | 1.7
100 | 2.7 | 2.7 | 5.4
For transmitters rated at a maximum output power not listed above, the recommended separation distance d in meters (m) can be determined using the equation applicable to the frequency of the transmitter, where P is the maximum output power rating of the transmitter in watts (W) according to the transmitter manufacturer.
NOTE 1: At 80 MHz and 800 MHz, the separation distance for the higher frequency range applies.
NOTE 2: These guidelines may not apply in all situations. Electromagnetic propagation is affected by absorption and reflection from structures, objects and people.

Safety Features and Fault Detection

Hardware Safety Features

Key hardware safety features include a watchdog timer circuit, motor driver and motor watchdog circuits, and a voltage detector circuit. Each safety circuit performs a unique function to insure the overall safety of the device.

Watchdog Timer Circuit

The microprocessor must send an appropriate signal to the watchdog circuit at least once per second. If the microprocessor does not, the watchdog circuit will time out and shut down the pump controller.

Watchdog timer circuitry is provided to monitor the status of the microprocessor and disable the motor and enable the audible alarm if the microprocessor fails to function properly. The microprocessor must strobe the watchdog circuit at least once every second in order to prevent the watchdog from performing its reset function. The reset output from the watchdog circuit is a pulse output. This acts to “jump startˮ the microprocessor. This unique feature allows the microprocessor to test the watchdog circuit on every power-up.

By setting a flag in the memory and not strobing the watchdog, the microprocessor can force a watchdog time-out. After being reset, the microprocessor checks the status flag to see if this was a time-out test. If so, the microprocessor continues normal power-up activities. If the reset occurred when the microprocessor was not expecting it, the microprocessor traps the event, sounds the audible alarm and displays an error message on the LCD.

Motor Driver/Motor Watchdog Circuit

Motor drive circuitry is composed of a series of power FET transistors, passive components, and 2 voltage comparators. Built into the motor drive circuitry is an RC timer which times how long the motor runs each time it is turned on. If the motor runs for more than an average of 3 seconds, the circuit will time out and disable the motor. A unique feature of this circuit is that control lines to and from the microprocessor circuit allow the microprocessor to perform a complete functional test of the motor drive circuit without running the motor. The microprocessor performs this test function every several minutes to assure its continued functionality. An input from the watchdog circuit prevents motor operation if the watchdog timer expires. The software verifies this function during the watchdog test described above.

Voltage Detector Circuit

Low voltage detection is performed by part of the watchdog circuit and by the microprocessor via software. Three low voltage levels are detected. The first 2 levels are detected by software and the third by hardware. The first level to be reached is the low battery warning threshold which occurs when the battery voltage decays to a nominal value of 2.4 volts when the motor is off or 1.8 volts when the motor is active. An analog to digital converter (ADC) built into the microprocessor allows the microprocessor, via software, to monitor the battery voltage. At the low battery warning threshold, the microprocessor enables a periodic series of beeps and displays a low battery warning message on the LCD. As the voltage operating the motor reaches a nominal value of 4.75 volts, the software disables delivery, places a battery depleted message on the LCD, and enables a constant two tone audible alarm. When the battery voltage decays to a nominal value of 1.0 volts, a hardware reset circuit is triggered which places the microprocessor in reset. This prevents ambiguous microprocessor operation when the battery voltage continues to decay. The hardware reset continues until the battery is completely discharged or until it is removed. Once the pump controller goes into low battery shutdown, only replacing the depleted batteries with new ones will clear the condition.

Software Safety Features

Hardware-related Software Safety Features

Program Memory Check

At power up and at regular intervals thereafter, the program memory is tested by calculating a cyclic redundancy code (CRC) on the program and then comparing it with the CRC stored with the program.

If the stored and calculated CRCs do not match, the software will display a system fault screen, turn on a continuous two-tone audible alarm, and stop all medication delivery.

RAM Memory Check

At power up, the random access memory is checked. A series of bit patterns is written to and read from each address in the RAM. If the read data is different from the written data, the software will display a system fault screen, turn on a continuous two-tone audible alarm, and stop all medication delivery.

Motor Circuit Check

At power up and at regular intervals thereafter, the motor circuit is checked to ensure that no power is being applied to the motor unless the motor is actually on. If the software detects power being applied to the motor at any other time, it will sound a continuous two-tone audible alarm and will no longer attempt to deliver medication. During every pump activation, the software checks to see whether the motor completes one activation. If the motor fails to turn, or fails to complete a cycle, the software will display a system fault screen, turn on a continuous two-tone audible alarm, and stop all medication delivery.

Keyboard Encoder Check

Every time the software receives data from the keyboard encoder, it is checked. If the data is not a valid key press, the software will disregard the key press. The keyboard is designed with redundant switches for

,

, and

. The software must detect that both switches are activated before taking any action.

Data Handling Software Safety Features

Data Stored in RAM

Before use, data associated with delivery and stored in RAM is tested by calculating a CRC on the data and then comparing it with the CRC stored with the data. If the stored and calculated CRCs do not match, the software will display a system fault screen, turn on a continuous two-tone audible alarm, and stop all medication delivery.

Data Stored in EEPROM

Before use, data associated with delivery and stored in EEPROM is tested by calculating a CRC on the data and then comparing it with the CRC stored with the data. If the stored and calculated CRCs do not match, the software will display a system fault screen, turn on a continuous two-tone audible alarm, and stop all medication delivery.

Data Stored in NOVRAM

Before use, data associated with delivery and stored in NOVRAM is tested by calculating a CRC on the data and then comparing it with the CRC stored with the data. If the stored and calculated CRCs do not match, the software will display a system fault screen, turn on a continuous two-tone audible alarm, and stop all medication delivery.

Data Used in Calculations

Calculations on data used in some way to control the delivery of medication are performed redundantly.

The two calculated values are then compared. If the two values do not match, the software will display a system fault screen, turn on a continuous two-tone audible alarm, and stop all medication delivery.

Timer Data Registers

The data in the real time clock is checked at regular intervals. If the data is not reasonable, the software will turn on a continuous two-tone audible alarm and stop all medication delivery.

Annual Functional Inspection

Smiths Medical recommends annual functional inspections and tests on the CADD-Legacy® 1400 pump. Contact Smiths Medical to coordinate return and inspection of the pump.

CAUTION: CADD-Legacy® 1400 pumps are sealed units. A broken or damaged seal will, therefore, be considered conclusive evidence that the pump has been misused and/or altered, which voids any and all warranties. All service and repair of CADD-Legacy® 1400 pumps must be performed by Smiths Medical or its authorized agents.

Collect Separately

This product contains electronic and other components (such as batteries) that may contain materials which, if disposed of with general household waste, could be damaging to the environment.

In accordance with Directive 2002/96/EC Waste Electrical and Electronic Equipment, Smiths Medical requires that residents of the European Union return this product for proper disposal at the end of its useful life.

If you are unsure of the proper disposal method, contact your local distributor for specific disposal instructions.

WARNING: There are potential health hazards associated with improper disposal of batteries, electronics, and contaminated (used) reservoirs and extension sets. Dispose of used batteries, reservoirs, extension sets and other used accessories, or a pump that has reached the end of its useful life, in an environmentally safe manner, and according to any regulations that may apply.

Limited Warranty

Smiths Medical ASD, Inc. (the “Manufacturer”) warrants to the Original Purchaser that the infusion pump (the “Pump”), not including accessories, shall be free from defects in materials and workmanship under normal use, if used in accordance with this Operator’s Manual, for a period of one year from the actual date of sale to the Original Purchaser. THERE ARE NO OTHER WARRANTIES.

This warranty does not cover normal wear and tear and maintenance items, and specifically excludes batteries, administration sets, extension sets or any other accessory items or equipment used with the Pump.

Subject to the conditions of and upon compliance with this Limited Warranty, the Manufacturer will repair or replace at its option without charge (except for a minimal charge for postage and handling) any Pump (not including accessories) which is defective if a claim is made during such one-year period.

The following conditions, procedures, and limitations apply to the Manufacturer’s obligation under this warranty:

A. Parties Covered by this Warranty: This warranty extends only to the Original Purchaser of the Pump. This warranty does not extend to subsequent purchasers. The Original Purchaser may be a patient, medical personnel, a hospital, or institution which purchases the Pump for treatment of patients. The Original Purchaser should retain the invoice or sales receipt as proof as to the actual date of purchase.

B. Warranty Performance Procedure: Notice of the claimed defect must be made in writing or by telephone to the Manufacturer as follows: Smiths Medical ASD, Inc. 1265 Grey Fox Road, St. Paul MN 55112 USA, 1 800.258.5361 (USA). Notice to the Manufacturer must include date of purchase, model and serial number, and a description of the claimed defect in sufficient detail to allow the Manufacturer to determine and facilitate any repairs which may be necessary. AUTHORIZATION MUST BE OBTAINED PRIOR TO RETURNING THE PUMP. If authorized, the Pump must be properly and carefully packaged and returned to the Manufacturer, postage prepaid. Any loss or damage during shipment is at the risk of the sender.

C. Conditions of Warranty: The warranty is void if the Pump has been 1) repaired by someone other than the Manufacturer or its authorized agent; 2) altered so that its stability or reliability is affected; 3) misused; or, 4) damaged by negligence or accident. Misuse includes, but is not limited to, use not in compliance with the Operator’s Manual or use with nonapproved accessories. The Pump is a sealed unit, and the fact that the seal has been broken will be considered conclusive evidence that the Pump has been altered or misused. Removal or damage to the Pump’s serial number will invalidate this warranty.

D. Limitations and Exclusions: Repair or replacement of the Pump or any component part thereof is the EXCLUSIVE remedy offered by the Manufacturer. The following exclusions and limitations shall apply:

1. No agent, representative, or employee of the Manufacturer has authority to bind the Manufacturer to any representation or warranty, expressed or implied.
2. THERE IS NO WARRANTY OF MERCHANTABILITY OR FITNESS OR USE OF THE PUMP FOR ANY PARTICULAR PURPOSE.
3. The Pump can only be used under the supervision of medical personnel whose skill and judgment determine the suitability of the Pump for any particular medical treatment.
4. All recommendations, information, and descriptive literature supplied by the Manufacturer or its agents are believed to be accurate and reliable, but do not constitute warranties.

E. Computer Program License:

1. The Pump is intended to be used in conjunction with a particular Licensed Computer Program supplied by Manufacturer and use of any other program or unauthorized modification of a Licensed Computer Program shall void Manufacturer’s warranty as set forth above.
2. The Original Purchaser and any users authorized by the Original Purchaser are hereby granted a nonexclusive, nontransferable license to use the Licensed Computer Program only in conjunction with the single Pump supplied by Manufacturer. The Licensed Computer Program is supplied only in machine-readable object code form and is based upon Manufacturer’s proprietary confidential information. No rights are granted under this license or otherwise to decompile, produce humanly readable copies of, reverse engineer, modify or create any derivative works based upon the Licensed Computer Program.
3. All other terms and conditions of this Limited Warranty shall apply to the Licensed Computer Program.
  The Manufacturer disclaims responsibility for the suitability of the Pump for any particular medical treatment or for any medical complications resulting from the use of the Pump. The Manufacturer shall not be responsible for any incidental damages or consequential damages to property, loss of profits, or loss of use caused by any defect or malfunction of the Pump.
  This warranty gives the Original Purchaser specific legal rights, and the Original Purchaser may have other legal rights which may vary from state to state.

Index

A

AC adapter

accessory jack

accuracy tests

AC indicator light

arrow keys

B

batteries, AA

installing

battery compartment

battery contacts, cleaning

battery, internal clock

battery life

biomed functions

extra dose lockout

morning dose lockout

specifications

upstream occlusion sensor on/off

biomed functions code

C

cassette latch

cleaning pump

continuous rate

programming

D

downstream occlusion sensor

E

ECG equipment, interference with

electromagnetic emissions and immunity declarations

extra dose

Lockout

programming

starting

stopping

extra dose key

G

given

clearing

K

keypad, keys

L

latch, cassette

lock level

changing

lock level code

M

magnetic resonance imaging

main screen

medication cassette reservoir

attaching

removing

morning dose

Lockout

starting

stopping

P

power jack

power-up

priming

programming

programming, general

programming screens

R

radiation, exposure to

reservoir volume

programming

resetting

S

safety features

hardware

software

security codes

biomed functions code

lock level code

service due

software version

specifications

biomed functions

delivery

general

standards

starting pump

stopping pump

symbols

system definition

T

turning pump on/off

U

ultrasound, vii

upstream occlusion sensor

W

warnings and cautions

warranty

Appendix A – Pump Programming Quick Reference for Healthcare Providers

This quick reference provides for step-by-step directions for several of the common pump programming tasks performed with the CADD-Legacy® 1400 pump. Additional pump information including warnings, cautions and more information on pump operations is located in the referenced sections of the pump Operator’s Manual. Please refer to the full prescribing information for DUOPA (carbidopa and levodopa) enteral suspension for indications and usage, contraindications, warnings, precautions, and adverse reactions.

Begin programming the pump by:

- Attaching a medication cassette reservoir
- Turning on the pump

For instruction on attaching a medication cassette reservoir, see Section 2, Pump Setup and Programming.

You will need the following items to complete these steps:

- Pump
- Medication cassette reservoir

Changing to Lock Level 0 (LL0)

Lock level 0 (LL0) allows the health care provider to adjust settings so they are appropriate for the patient. For more information on lock levels descriptions, see Section 1, General Description. For more information on changing the lock level, see Section 2, Pump Setup and Programming.

**Text Omitted**

Pump Programming Settings

Program the pump settings to customize the medication delivery inputs for the patient. For more information see Section 2, Pump Setup and Programming.

NOTE: Ensure that the pump is in lock level 0 (LL0) and

appears on the screen.

1. Press

Check for

on the screen.

NOTE: Not in Use is the default setting for the reservoir volume. The reservoir volume feature is not required for use, but is available at provider discretion.

2. Press

again. Check for

on the screen.

3. Press

or

to select the desired continuous rate.

4. Press

Pump Status: The continuous rate is now set.

5. Press

Check for

on the screen.

6. Press

or

to select the extra dose amount.

7. Press

Pump Status: The extra dose amount is now set.

8. Press

check for

on the screen

9. Press

if you wish to clear the amount given.

10. Press

NOTE: To change a setting again, press NEXT until the appropriate screen appears. Press

or

to adjust the setting, then press

to confirm.

Changing Lockout Times

Program the dose lockout times to customize medication delivery inputs for each patient. Lockout times will determine how often a patient can deliver a morning dose and an extra dose. These values should be determined during titration. For more information on DUOPA titration, refer to the full prescribing information for DUOPA (carbidopa and levodopa) enteral suspension.

The biomed functions allow the health care provider access to the extra dose lockout and morning dose lockout settings. For more information about biomed functions, see Section 4, Biomed Functions.

NOTE:

- Ensure that the pump is in lock level 0 (LL0) and

is on the screen.

- When entering a new lockout value, any lockout time previously in effect will be cleared.

**Text Omitted**

Programming the Morning Dose

Program the morning dose to customize medication delivery for the patient. For more information, see Section 2, Pump Setup and Programming.

CAUTION: Review programming screens when complete to make sure desired programming has been entered. Check to make sure unintended changes were not made to the morning dose, continuous rate, or extra dose volume. If unintended changes were made, go to the appropriate screen and program the desired value.

1. The pump must be running with a cassette attached and in LL0 or LL1. Start the pump, if necessary and confirm the lock level settings.

NOTE: In LL0, programming in the full range is possible. In LL1, you can program up to the LL0 value.

2. Press

should appear on the screen.

3. Press

or

to select the desired morning dose volume.

4. Press

to store the morning dose volume.

Setting the Lock Level

For patient use, the pump must be set to lock level 2 (LL2) or lock level 1 (LL1). For more information on lock levels descriptions, see Section 1, General Description. For more information on changing the lock level, see Section 2, Pump Setup and Programming.

**Text Omitted**

Manufacturer:
Smiths Medical ASD, Inc.
1265 Grey Fox Road
St. Paul, MN 55112 USA
Tel: 1 800 258 5361 (USA), +1 614 210 7300
www.smiths-medical.com

CADD, CADD-Legacy, and Smiths Medical design mark are trademarks of Smiths Medical. The symbol ® indicates the trademark is registered in the U.S. Patent and Trademark Office and certain other countries. All other names and marks mentioned are the trade names, trademarks or service marks of their respective owners.

© 2015 Smiths Medical. All rights reserved.

2015-01
40-6756-01C

PACKAGE LABEL

NDC 0074-3012-07

Duopa®

carbidopa and levodopa
enteral suspension

4.63 mg / 20 mg per mL

7 Cassettes (100 mL each)

THIS PACKAGE NOT INTENDED FOR
HOUSEHOLDS WITH YOUNG CHILDREN

Each mL contains 5 mg of carbidopa monohydrate

(equivalent to 4.63 mg of carbidopa anhydrous) and 20 mg of levodopa.

Pharmacist: Store frozen.
Thaw in refrigerator prior to dispensing.

See package insert for full prescribing information.

Store in the refrigerator between 36°-46°F (2°-8°C).

Protect from light.

Store cassettes in the carton until use.

Rx only

abbvie